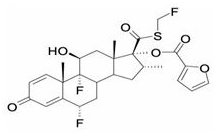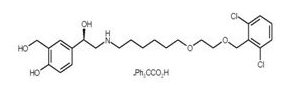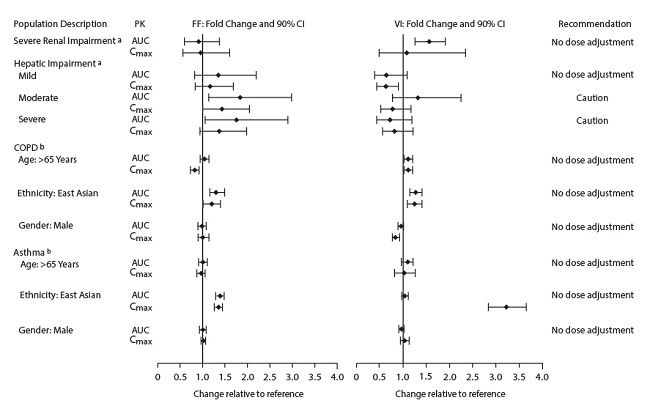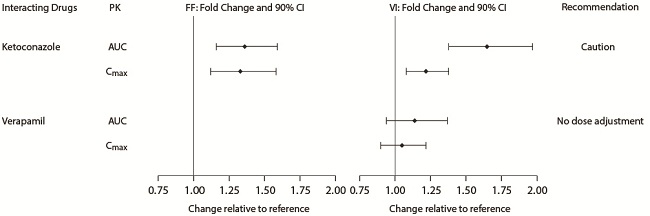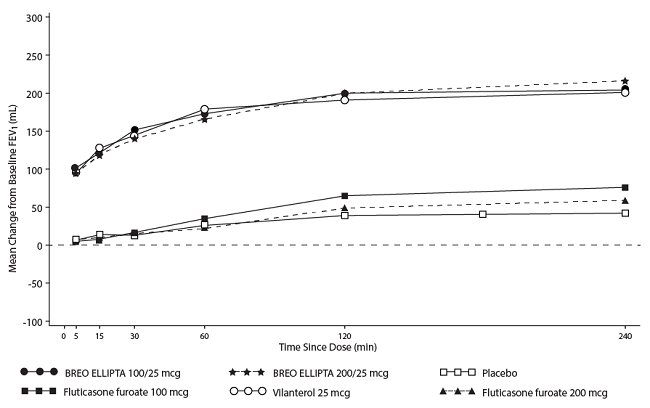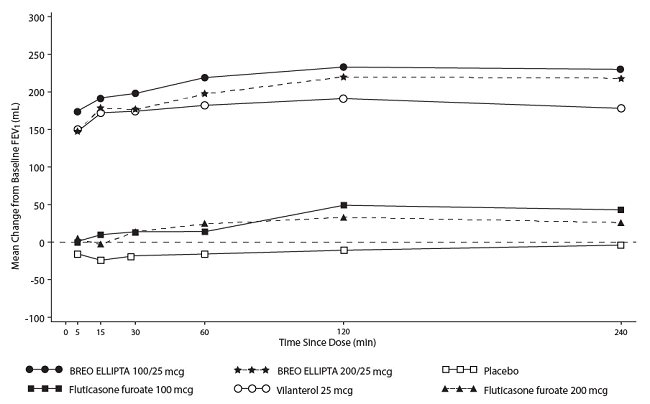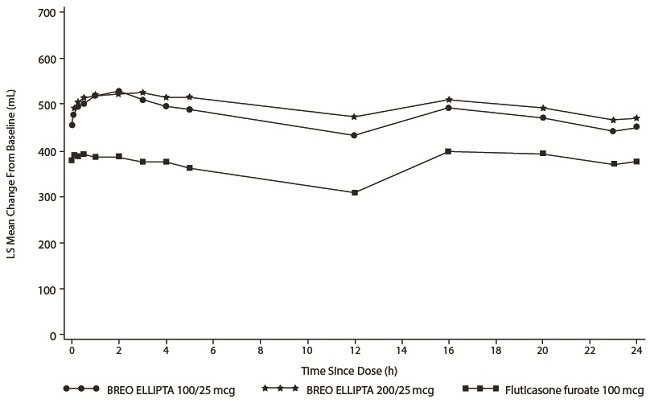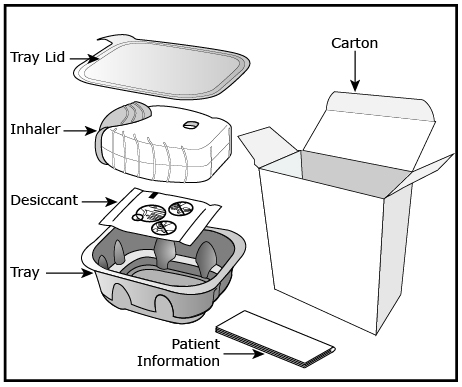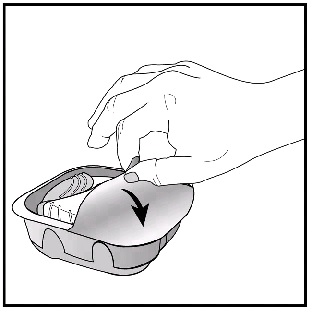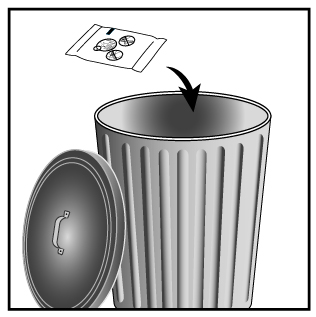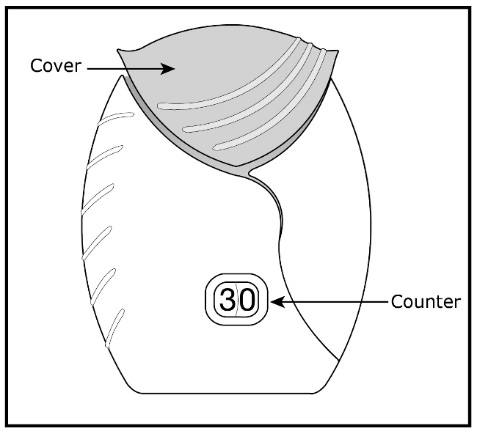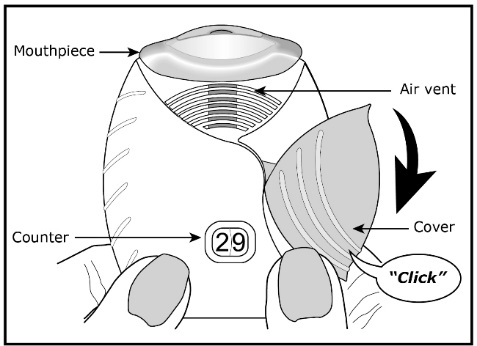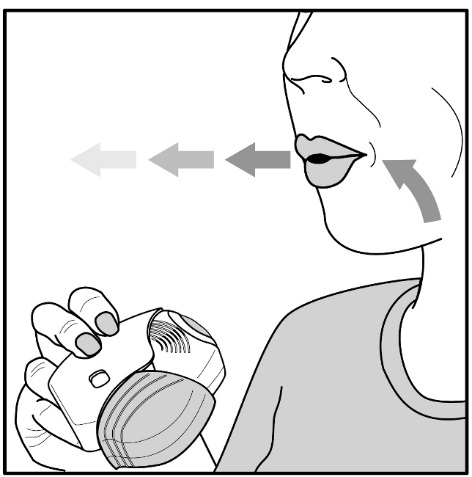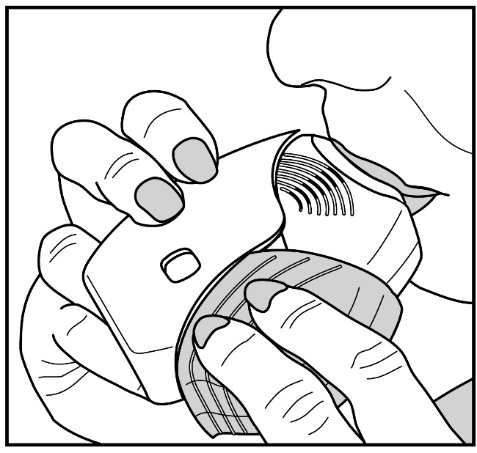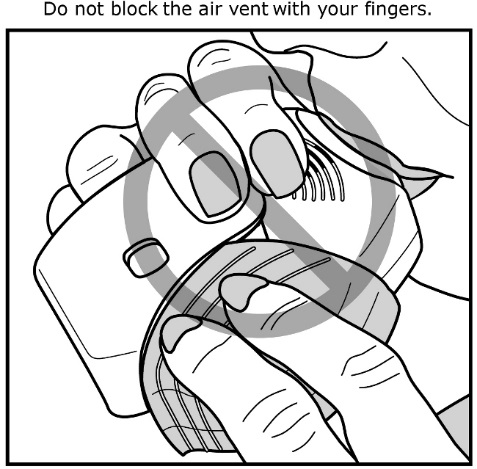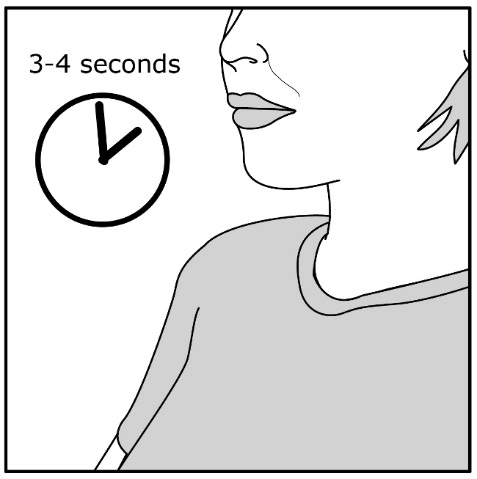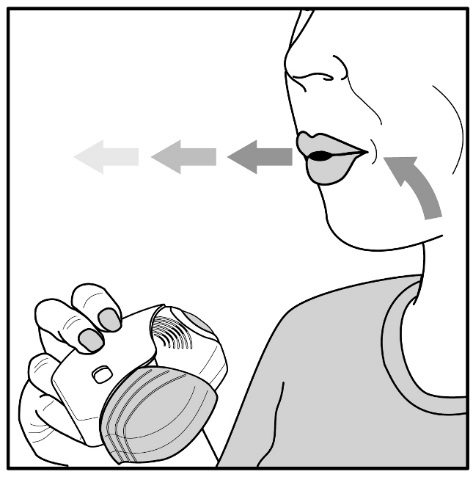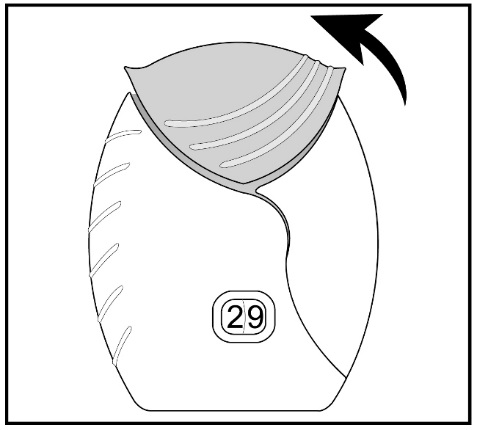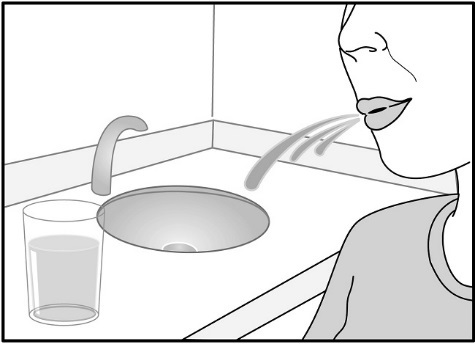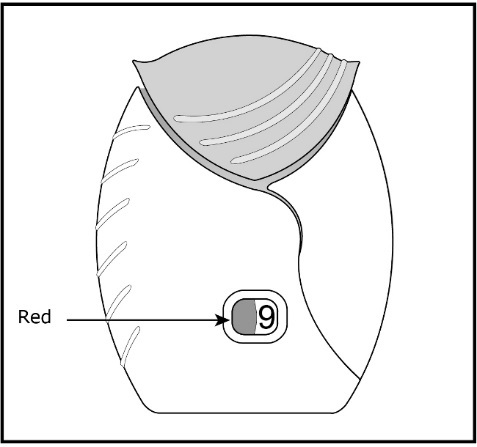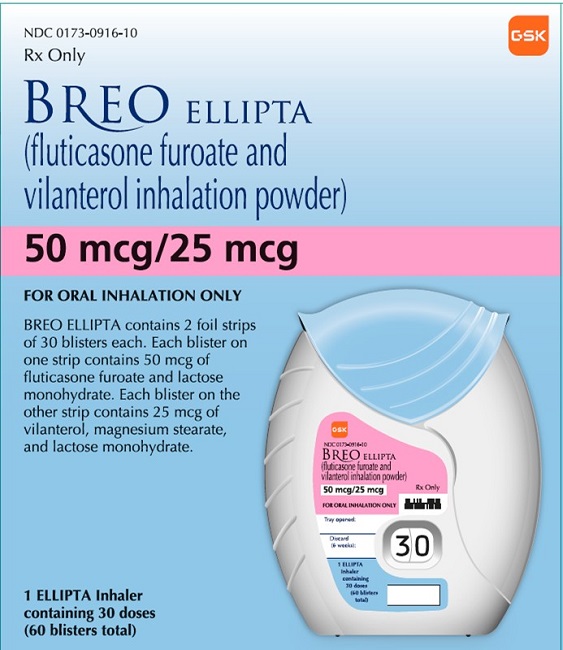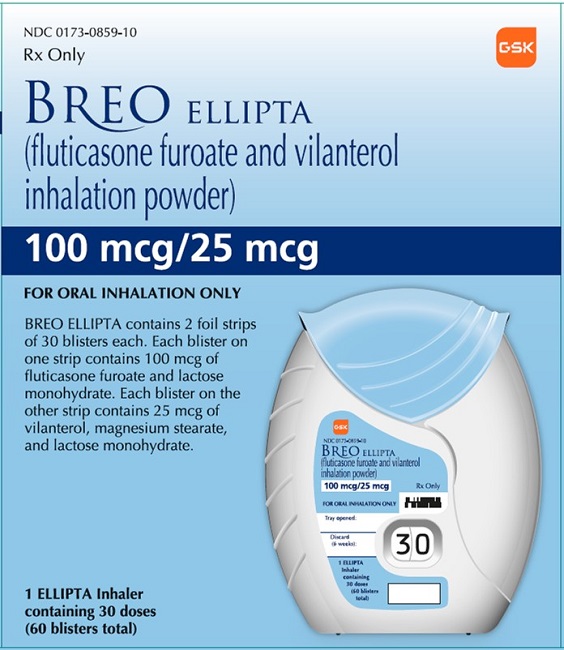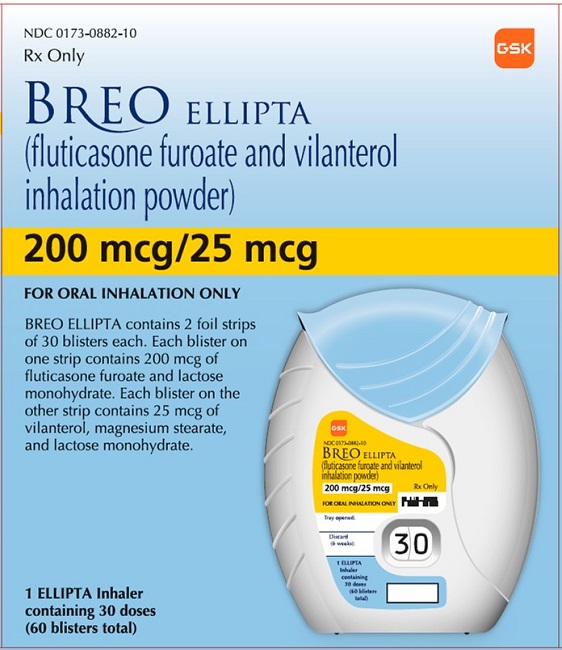 DRUG LABEL: Breo Ellipta
NDC: 0173-0916 | Form: POWDER
Manufacturer: GlaxoSmithKline LLC
Category: prescription | Type: HUMAN PRESCRIPTION DRUG LABEL
Date: 20241107

ACTIVE INGREDIENTS: FLUTICASONE FUROATE 50 ug/1 1; VILANTEROL TRIFENATATE 25 ug/1 1
INACTIVE INGREDIENTS: LACTOSE MONOHYDRATE; MAGNESIUM STEARATE

HIGHLIGHTS OF PRESCRIBING INFORMATION

These highlights do not include all the information needed to use BREO ELLIPTA safely and effectively. See full prescribing information for BREO ELLIPTA.
BREO ELLIPTA (fluticasone furoate and vilanterol inhalation powder), for oral inhalation use
Initial U.S. Approval: 2013

1 INDICATIONS AND USAGE

BREO ELLIPTA is a combination of fluticasone furoate, a corticosteroid, and vilanterol, a long-acting beta2-adrenergic agonist (LABA), indicated for:

- the maintenance treatment of patients with chronic obstructive pulmonary disease (COPD). (1.1)
- the maintenance treatment of asthma in patients aged 5 years and older. (1.2)

Limitations of Use: Not indicated for relief of acute bronchospasm. (1.3, 5.2)

2 DOSAGE AND ADMINISTRATION

- For oral inhalation only. (2.3)
- Maintenance treatment of COPD: 1 actuation of BREO ELLIPTA 100/25 mcg once daily administered by oral inhalation. (2.1)
- Maintenance treatment of asthma in adult patients aged 18 years and older: 1 actuation of BREO ELLIPTA 100/25 mcg or BREO ELLIPTA 200/25 mcg once daily administered by oral inhalation. (2.2)
- Maintenance treatment of asthma in pediatric patients aged 12 to 17 years: 1 actuation of BREO ELLIPTA 100/25 mcg once daily administered by oral inhalation. (2.2)
- Maintenance treatment of asthma in pediatric patients aged 5 to 11 years: 1 actuation of BREO ELLIPTA 50/25 mcg once daily administered by oral inhalation. (2.2)

3 DOSAGE FORMS AND STRENGTHS

Inhalation powder:

- 50 mcg fluticasone furoate and 25 mcg vilanterol (50/25 mcg) per actuation (3)
- 100 mcg fluticasone furoate and 25 mcg vilanterol (100/25 mcg) per actuation (3)
- 200 mcg fluticasone furoate and 25 mcg vilanterol (200/25 mcg) per actuation (3)

4 CONTRAINDICATIONS

- Primary treatment of status asthmaticus or acute episodes of COPD or asthma requiring intensive measures. (4)
- Severe hypersensitivity to milk proteins or any ingredients. (4)

5 WARNINGS AND PRECAUTIONS

- LABA monotherapy increases the risk of serious asthma-related events. (5.1)
- Do not initiate in acutely deteriorating COPD or asthma. Do not use to treat acute symptoms. (5.2)
- Do not use in combination with additional therapy containing a LABA because of risk of overdose. (5.3)
- Candida albicans infection of the mouth and pharynx may occur. Monitor patients periodically. Advise the patient to rinse his/her mouth with water without swallowing after inhalation to help reduce the risk. (5.4)
- Increased risk of pneumonia in patients with COPD. Monitor patients for signs and symptoms of pneumonia. (5.5)
- Potential worsening of infections (e.g., existing tuberculosis; fungal, bacterial, viral, or parasitic infections; ocular herpes simplex). Use with caution in patients with these infections. More serious or even fatal course of chickenpox or measles can occur in susceptible patients. (5.6)
- Risk of impaired adrenal function when transferring from systemic corticosteroids. Wean patients slowly from systemic corticosteroids if transferring to BREO ELLIPTA. (5.7)
- Hypercorticism and adrenal suppression may occur with very high dosages or at the regular dosage in susceptible individuals. If such changes occur, discontinue BREO ELLIPTA slowly. (5.8)
- If paradoxical bronchospasm occurs, discontinue BREO ELLIPTA and institute alternative therapy. (5.10)
- Use with caution in patients with cardiovascular disorders because of beta-adrenergic stimulation. (5.12)
- Assess for decrease in bone mineral density (BMD) initially and periodically thereafter. (5.13)
- Monitor growth of pediatric patients (5.14)
- Glaucoma and cataracts may occur with long-term use of Inhaled Corticosteroid (ICS). Consider referral to an ophthalmologist in patients who develop ocular symptoms or use BREO ELLIPTA long term. (5.15)
- Use with caution in patients with convulsive disorders, thyrotoxicosis, diabetes mellitus, and ketoacidosis. (5.16)
- Increased blood glucose levels have been reported. Also, be alert to hypokalemia. (5.17)

6 ADVERSE REACTIONS

- COPD: Most common adverse reactions (incidence ≥3%) are nasopharyngitis, upper respiratory tract infection, headache, oral candidiasis, back pain, pneumonia, bronchitis, sinusitis, cough, oropharyngeal pain, arthralgia, hypertension, influenza, pharyngitis, and pyrexia. (6.1)
- Asthma: Most common adverse reactions (incidence ≥2%) are nasopharyngitis, oral candidiasis, headache, influenza, upper respiratory tract infection, bronchitis, sinusitis, oropharyngeal pain, dysphonia, and cough. (6.2)

To report SUSPECTED ADVERSE REACTIONS, contact GlaxoSmithKline at 1-888-825-5249 or FDA at 1-800-FDA-1088 or www.fda.gov/medwatch.

7 DRUG INTERACTIONS

- Strong cytochrome P450 3A4 inhibitors (e.g., ketoconazole): Use with caution. May cause systemic corticosteroid and cardiovascular effects. (7.1)
- Monoamine oxidase inhibitors and tricyclic antidepressants: Use with extreme caution. May potentiate effect of vilanterol on cardiovascular system. (7.2)
- Beta-blockers: Use with caution. May block bronchodilatory effects of beta-agonists and produce severe bronchospasm. (7.3)
- Diuretics: Use with caution. Electrocardiographic changes and/or hypokalemia associated with non–potassium-sparing diuretics may worsen with concomitant beta-agonists. (7.4)

8 USE IN SPECIFIC POPULATIONS

Hepatic impairment: Fluticasone furoate systemic exposure may increase in patients with moderate or severe impairment. Monitor for systemic corticosteroid effects. (8.6, 12.3)

FULL PRESCRIBING INFORMATION

1 INDICATIONS AND USAGE

1.1 Maintenance Treatment of Chronic Obstructive Pulmonary Disease

BREO ELLIPTA is indicated for the maintenance treatment of patients with chronic obstructive pulmonary disease (COPD).

1.2 Maintenance Treatment of Asthma

BREO ELLIPTA is indicated for the maintenance treatment of asthma in patients aged 5 years and older.

1.3 Limitations of Use

BREO ELLIPTA is NOT indicated for the relief of acute bronchospasm.

2 DOSAGE AND ADMINISTRATION

2.1 Recommended Dosage for Maintenance Treatment of Chronic Obstructive Pulmonary Disease

The recommended dosage of BREO ELLIPTA 100/25 mcg (containing fluticasone furoate 100 mcg and vilanterol 25 mcg) is 1 actuation once daily by oral inhalation.

If shortness of breath occurs in the period between doses, an inhaled, short-acting beta2-agonist (rescue medicine, e.g., albuterol) should be used for immediate relief.

2.2 Recommended Dosage for Maintenance Treatment of Asthma

Adult Patients Aged 18 Years and Older

The recommended dosage of BREO ELLIPTA 100/25 mcg (containing fluticasone furoate 100 mcg and vilanterol 25 mcg) is 1 actuation once daily by oral inhalation or BREO ELLIPTA 200/25 mcg (containing fluticasone furoate 200 mcg and vilanterol 25 mcg) is 1 actuation once daily by oral inhalation.

- When choosing the starting dosage strength of BREO ELLIPTA, consider the patients’ disease severity, their previous asthma therapy, including the inhaled corticosteroid (ICS) dosage, as well as the patients’ current control of asthma symptoms and risk of future exacerbation.
- The median time to onset, defined as a 100-mL increase from baseline in mean forced expiratory volume in 1 second (FEV1), was approximately 15 minutes after beginning treatment. Individual patients will experience a variable time to onset and degree of symptom relief.
- For patients who do not respond adequately to BREO ELLIPTA 100/25 mcg once daily, increasing the dose to BREO ELLIPTA 200/25 mcg once daily may provide additional improvement in asthma control. For patients who do not respond adequately to BREO ELLIPTA 200/25 mcg once daily, re-evaluate and consider other therapeutic regimens and additional therapeutic options.
- The maximum recommended dosage is 1 inhalation of BREO ELLIPTA 200/25 mcg once daily.
- If asthma symptoms arise in the period between doses, an inhaled, short-acting beta2-agonist (rescue medicine, e.g., albuterol) should be used for immediate relief.

Pediatric Patients Aged 12 to 17 Years

The recommended dosage of BREO ELLIPTA 100/25 mcg (containing fluticasone furoate 100 mcg and vilanterol 25 mcg) is 1 actuation once daily by oral inhalation [see Warnings and Precautions (5.14)].

Pediatric Patients Aged 5 to 11 Years

The recommended dosage of BREO ELLIPTA 50/25 mcg (containing fluticasone furoate 50 mcg and vilanterol 25 mcg) is 1 actuation once daily by oral inhalation [see Warnings and Precautions (5.14)].

2.3 Administration Information

- After inhalation, the patient should rinse his/her mouth with water without swallowing to help reduce the risk of oropharyngeal candidiasis [see Warnings and Precautions (5.4)].
- BREO ELLIPTA should be used at the same time every day. Do not use BREO ELLIPTA more than 1 time every 24 hours.
- More frequent administration or a greater number of inhalations (more than 1 inhalation daily) of the prescribed strength of BREO ELLIPTA is not recommended as some patients are more likely to experience adverse effects with higher doses.

3 DOSAGE FORMS AND STRENGTHS

Inhalation powder:

- 50 mcg fluticasone furoate and 25 mcg vilanterol (50/25 mcg) per actuation
- 100 mcg fluticasone furoate and 25 mcg vilanterol (100/25 mcg) per actuation
- 200 mcg fluticasone furoate and 25 mcg vilanterol (200/25 mcg) per actuation

4 CONTRAINDICATIONS

BREO ELLIPTA is contraindicated in the following conditions:

- Primary treatment of status asthmaticus or other acute episodes of COPD or asthma where intensive measures are required [see Warnings and Precautions (5.2)].
- Severe hypersensitivity to milk proteins or demonstrated hypersensitivity to fluticasone furoate, vilanterol, or any of the excipients [see Warnings and Precautions (5.11), Description (11)].

5 WARNINGS AND PRECAUTIONS

5.1 Serious Asthma-Related Events – Hospitalizations, Intubations, Death

Use of Long-acting Beta2-adrenergic Agonist (LABA) as monotherapy (without ICS) for asthma is associated with an increased risk of asthma-related death [see Salmeterol Multicenter Asthma Research Trial (SMART)]. Available data from controlled clinical trials also suggest that use of LABA as monotherapy increases the risk of asthma-related hospitalization in pediatric patients. These findings are considered a class effect of LABA monotherapy. When LABA are used in fixed-dose combination with ICS, data from large clinical trials do not show a significant increase in the risk of serious asthma‑related events (hospitalizations, intubations, death) compared with ICS alone (see Serious Asthma-Related Events with Inhaled Corticosteroid/Long-Acting Beta2-Adrenergic Agonists).

Serious Asthma-Related Events with Inhaled Corticosteroid/Long-Acting Beta2-Adrenergic Agonists

Four (4) large, 26-week, randomized, double-blind, active-controlled clinical safety trials were conducted to evaluate the risk of serious asthma-related events when LABA were used in fixed-dose combination with ICS compared with ICS alone in patients with asthma. Three (3) trials included adult and pediatric patients aged 12 years and older: 1 trial compared budesonide/formoterol with budesonide, 1 trial compared fluticasone propionate/salmeterol inhalation powder with fluticasone propionate inhalation powder, and 1 trial compared mometasone furoate/formoterol with mometasone furoate. The fourth trial included pediatric patients aged 4 to 11 years and compared fluticasone propionate/salmeterol inhalation powder with fluticasone propionate inhalation powder. The primary safety endpoint for all 4 trials was serious asthma-related events (hospitalizations, intubations, death). A blinded adjudication committee determined whether events were asthma related.

The 3 adult and pediatric trials were designed to rule out a risk margin of 2.0, and the pediatric trial was designed to rule out a risk margin of 2.7. Each individual trial met its pre-specified objective and demonstrated non-inferiority of ICS/LABA to ICS alone. A meta-analysis of the 3 adult and pediatric trials did not show a significant increase in risk of a serious asthma-related event with ICS/LABA fixed-dose combination compared with ICS alone (Table 1). These trials were not designed to rule out all risk for serious asthma-related events with ICS/LABA compared with ICS.

Table 1. Meta-Analysis of Serious Asthma-Related Events in Patients with Asthma Aged 12 Years and Older
 | ICS/LABA; (n = 17,537)a | ICS; (n = 17,552)a | ICS/LABA vs. ICS; Hazard Ratio (95% CI)b
Serious asthma-related eventc | 116 | 105 | 1.10 (0.85, 1.44)
Asthma-related death | 2 | 0
Asthma-related intubation (endotracheal) | 1 | 2
Asthma-related hospitalization (≥24-hour stay) | 115 | 105
ICS = Inhaled Corticosteroid, LABA = Long-acting Beta2-adrenergic Agonist.
a Randomized patients who had taken at least 1 dose of study drug. Planned treatment used for analysis.
b Estimated using a Cox proportional hazards model for time to first event with baseline hazards stratified by each of the 3 trials.
c Number of patients with event that occurred within 6 months after the first use of study drug or 7 days after the last date of study drug, whichever date was later. Patients can have one or more events, but only the first event was counted for analysis. A single, blinded, independent adjudication committee determined whether events were asthma related.

The pediatric safety trial included 6,208 pediatric patients aged 4 to 11 years who received ICS/LABA (fluticasone propionate/salmeterol inhalation powder) or ICS (fluticasone propionate inhalation powder). In this trial, 27/3,107 (0.9%) patients randomized to ICS/LABA and 21/3,101 (0.7%) patients randomized to ICS experienced a serious asthma-related event. There were no asthma-related deaths or intubations. ICS/LABA did not show a significantly increased risk of a serious asthma-related event compared with ICS based on the pre-specified risk margin (2.7), with an estimated hazard ratio of time to first event of 1.29 (95% CI: 0.73, 2.27).

Salmeterol Multicenter Asthma Research Trial (SMART)

A 28-week, placebo-controlled, U.S. trial that compared the safety of salmeterol with placebo, each added to usual asthma therapy, showed an increase in asthma-related deaths in patients receiving salmeterol (13/13,176 in patients treated with salmeterol vs. 3/13,179 in patients treated with placebo; relative risk: 4.37 [95% CI: 1.25, 15.34]). Use of background ICS was not required in SMART. The increased risk of asthma-related death is considered a class effect of LABA monotherapy.

5.2 Deterioration of Disease and Acute Episodes

BREO ELLIPTA should not be initiated in patients during rapidly deteriorating or potentially life-threatening episodes of COPD or asthma. BREO ELLIPTA has not been studied in patients with acutely deteriorating COPD or asthma. The initiation of BREO ELLIPTA in this setting is not appropriate.

In COPD, if BREO ELLIPTA 100/25 mcg no longer controls symptoms of bronchoconstriction; the patient’s inhaled, short-acting, beta2-agonist becomes less effective; or the patient needs more short-acting beta2-agonist than usual, these may be markers of deterioration of disease. In this setting, re-evaluate the patient and the COPD treatment regimen at once. For COPD, the daily dose of BREO ELLIPTA 100/25 mcg should not be increased.

Increasing use of inhaled, short-acting beta2-agonists is a marker of deteriorating asthma. In this situation, the patient requires immediate reevaluation with reassessment of the treatment regimen, giving special consideration to the need for additional therapeutic options. Patients should not use more than 1 inhalation once daily of BREO ELLIPTA.

BREO ELLIPTA should not be used for the relief of acute symptoms, i.e., as rescue therapy for the treatment of acute episodes of bronchospasm. BREO ELLIPTA has not been studied in the relief of acute symptoms and extra doses should not be used for that purpose. Acute symptoms should be treated with an inhaled, short-acting beta2-agonist.

When beginning treatment with BREO ELLIPTA, patients who have been taking oral or inhaled, short-acting beta2-agonists on a regular basis (e.g., 4 times a day) should be instructed to discontinue the regular use of these drugs and to use them only for symptomatic relief of acute respiratory symptoms. When prescribing BREO ELLIPTA, the healthcare provider should also prescribe an inhaled, short-acting beta2-agonist and instruct the patient on how it should be used.

5.3 Risk Associated with Excessive Use of Long-Acting Beta2-Agonists, including BREO ELLIPTA

BREO ELLIPTA should not be used more often than recommended, at higher doses than recommended [see Dosage and Administration (2)], or in conjunction with other therapies containing LABA, as an overdose may result. Clinically significant cardiovascular effects and fatalities have been reported in association with excessive use of inhaled sympathomimetic drugs. Patients using BREO ELLIPTA should not use another therapy containing a LABA (e.g., salmeterol, formoterol fumarate, arformoterol tartrate, indacaterol) for any reason.

5.4 Oropharyngeal Candidiasis

BREO ELLIPTA contains fluticasone furoate, an ICS. Localized infections of the mouth and pharynx with Candida albicans have occurred in patients treated with orally inhaled drug products containing fluticasone furoate. Monitor patients periodically. When such an infection develops, it should be treated with appropriate local or systemic (i.e., oral) antifungal therapy while treatment with BREO ELLIPTA continues. In some cases, therapy with BREO ELLIPTA may need to be interrupted. Advise the patient to rinse his/her mouth with water without swallowing following administration of BREO ELLIPTA to help reduce the risk of oropharyngeal candidiasis.

5.5 Pneumonia

An increase in the incidence of pneumonia has been observed in patients with COPD receiving BREO ELLIPTA 100/25 mcg in clinical trials. There was also an increased incidence of pneumonias resulting in hospitalization. In some incidences these pneumonia events were fatal. Healthcare providers should remain vigilant for the possible development of pneumonia in patients with COPD as clinical features of pneumonia and exacerbations frequently overlap.

In replicate 12-month trials in 3,255 patients with moderate to severe COPD who had experienced a COPD exacerbation in the previous year, there was a higher incidence of pneumonia reported in patients receiving fluticasone furoate/vilanterol 50/25 mcg: 6% (48 of 820 patients); BREO ELLIPTA 100/25 mcg: 6% (51 of 806 patients); or BREO ELLIPTA 200/25 mcg: 7% (55 of 811 patients) than in patients receiving vilanterol 25 mcg: 3% (27 of 818 patients). There was no fatal pneumonia in patients receiving vilanterol or fluticasone furoate/vilanterol 50/25 mcg. There was fatal pneumonia in 1 patient receiving BREO ELLIPTA 100/25 mcg and in 7 patients receiving BREO ELLIPTA 200/25 mcg (<1% for each treatment group).

In a mortality trial with a median treatment duration of 1.5 years in 16,568 patients with moderate COPD and cardiovascular disease, the annualized incidence rate of pneumonia was 3.4 per 100 patient-years for BREO ELLIPTA 100/25 mcg, 3.2 for placebo, 3.3 for fluticasone furoate 100 mcg, and 2.3 for vilanterol 25 mcg. Adjudicated, on-treatment deaths due to pneumonia occurred in 13 patients receiving BREO ELLIPTA 100/25 mcg, 9 patients receiving placebo, 10 patients receiving fluticasone furoate 100 mcg, and 6 patients receiving vilanterol 25 mcg (<0.2 per 100 patient-years for each treatment group).

5.6 Immunosuppression and Risk of Infections

Patients who are on drugs that suppress the immune system are more susceptible to infection than healthy individuals. Chickenpox and measles can have a more serious or even fatal course in susceptible patients using corticosteroids. In such patients who have not had these diseases or been properly immunized, particular care should be taken to avoid exposure. How the dose, route, and duration of corticosteroid administration affect the risk of developing a disseminated infection is not known. The contribution of the underlying disease and/or prior corticosteroid treatment to the risk is also not known. If a patient is exposed to chickenpox, prophylaxis with varicella zoster immune globulin (VZIG) may be indicated. If a patient is exposed to measles, prophylaxis with pooled intramuscular immunoglobulin (IG) may be indicated. (See the respective Prescribing Information for VZIG and IG) If chickenpox develops, treatment with antiviral agents may be considered.

ICS should be used with caution, if at all, in patients with active or quiescent tuberculosis infections of the respiratory tract; systemic fungal, bacterial, viral, or parasitic infections; or ocular herpes simplex.

5.7 Transferring Patients from Systemic Corticosteroid Therapy

Hypothalamic-Pituitary-Adrenal Suppression/Adrenal Insufficiency

Particular care is needed for patients who have been transferred from systemically active corticosteroids to ICS because deaths due to adrenal insufficiency have occurred in patients during and after transfer from systemic corticosteroids to less systemically available ICS. After withdrawal from systemic corticosteroids, a number of months are required for recovery of hypothalamic-pituitary-adrenal (HPA) function.

Patients who have been previously maintained on 20 mg or more of prednisone (or its equivalent) may be most susceptible, particularly when their systemic corticosteroids have been almost completely withdrawn. During this period of HPA suppression, patients may exhibit signs and symptoms of adrenal insufficiency when exposed to trauma, surgery, or infection (particularly gastroenteritis) or other conditions associated with severe electrolyte loss. Although BREO ELLIPTA may control COPD or asthma symptoms during these episodes, in recommended doses it supplies less than normal physiological amounts of glucocorticoid systemically and does NOT provide the mineralocorticoid activity that is necessary for coping with these emergencies.

During periods of stress, a severe COPD exacerbation, or a severe asthma attack, patients who have been withdrawn from systemic corticosteroids should be instructed to resume oral corticosteroids (in large doses) immediately and to contact their healthcare practitioner for further instruction. These patients should also be instructed to carry a warning card indicating that they may need supplementary systemic corticosteroids during periods of stress, a severe COPD exacerbation, or a severe asthma attack.

Patients requiring oral corticosteroids should be weaned slowly from systemic corticosteroid use after transferring to BREO ELLIPTA. Prednisone reduction can be accomplished by reducing the daily prednisone dose by 2.5 mg on a weekly basis during therapy with BREO ELLIPTA. Lung function (FEV1 or peak expiratory flow), beta-agonist use, and COPD or asthma symptoms should be carefully monitored during withdrawal of oral corticosteroids. In addition, patients should be observed for signs and symptoms of adrenal insufficiency, such as fatigue, lassitude, weakness, nausea and vomiting, and hypotension.

Unmasking of Allergic Conditions Previously Suppressed by Systemic Corticosteroids

Transfer of patients from systemic corticosteroid therapy to BREO ELLIPTA may unmask allergic conditions previously suppressed by the systemic corticosteroid therapy (e.g., rhinitis, conjunctivitis, eczema, arthritis, eosinophilic conditions).

Corticosteroid Withdrawal Symptoms

During withdrawal from oral corticosteroids, some patients may experience symptoms of systemically active corticosteroid withdrawal (e.g., joint and/or muscular pain, lassitude, depression) despite maintenance or even improvement of respiratory function.

5.8 Hypercorticism and Adrenal Suppression

Inhaled fluticasone furoate is absorbed into the circulation and can be systemically active. Effects of fluticasone furoate on the HPA axis are not observed with the therapeutic doses of fluticasone furoate in BREO ELLIPTA. However, exceeding the recommended dosage or coadministration with a strong cytochrome P450 3A4 (CYP3A4) inhibitor may result in HPA dysfunction [see Warnings and Precautions (5.9), Drug Interactions (7.1)].

Because of the possibility of significant systemic absorption of ICS in sensitive patients, patients treated with BREO ELLIPTA should be observed carefully for any evidence of systemic corticosteroid effects. Particular care should be taken in observing patients postoperatively or during periods of stress for evidence of inadequate adrenal response.

It is possible that systemic corticosteroid effects such as hypercorticism and adrenal suppression (including adrenal crisis) may appear in a small number of patients who are sensitive to these effects. If such effects occur, reduce the dose of BREO ELLIPTA slowly, consistent with accepted procedures for reducing systemic corticosteroids, and consider other treatments for management of COPD or asthma symptoms.

5.9 Drug Interactions with Strong Cytochrome P450 3A4 Inhibitors

Caution should be exercised when considering the coadministration of BREO ELLIPTA with ketoconazole and other known strong CYP3A4 inhibitors (including, but not limited to, ritonavir, clarithromycin, conivaptan, indinavir, itraconazole, lopinavir, nefazodone, nelfinavir, saquinavir, telithromycin, troleandomycin, voriconazole) because increased systemic corticosteroid and increased cardiovascular adverse effects may occur [see Drug Interactions (7.1), Clinical Pharmacology (12.3)].

5.10 Paradoxical Bronchospasm

BREO ELLIPTA can produce paradoxical bronchospasm, which may be life threatening. If paradoxical bronchospasm occurs following dosing with BREO ELLIPTA, it should be treated immediately with an inhaled, short-acting bronchodilator; BREO ELLIPTA should be discontinued immediately; and alternative therapy should be instituted [see Adverse Reactions (6.3)].

5.11 Hypersensitivity Reactions, including Anaphylaxis

Hypersensitivity reactions such as anaphylaxis, angioedema, rash, and urticaria may occur after administration of BREO ELLIPTA. Discontinue BREO ELLIPTA if such reactions occur. There have been reports of anaphylactic reactions in patients with severe milk protein allergy after inhalation of other powder medications containing lactose; therefore, patients with severe milk protein allergy should not use BREO ELLIPTA [see Contraindications (4), Adverse Reactions (6.3)].

5.12 Cardiovascular Effects

BREO ELLIPTA, like other drugs containing beta2-agonists, can produce a clinically significant cardiovascular effect in some patients as measured by increases in pulse rate, systolic or diastolic blood pressure, and also cardiac arrhythmias, such as supraventricular tachycardia and extrasystoles [see Adverse Reactions (6.3)]. If such effects occur, BREO ELLIPTA may need to be discontinued. In addition, beta-agonists have been reported to produce electrocardiographic changes, such as flattening of the T wave, prolongation of the QTc interval, and ST segment depression, although the clinical significance of these findings is unknown [see Clinical Pharmacology (12.2)]. Fatalities have been reported in association with excessive use of inhaled sympathomimetic drugs.

In healthy subjects, large doses of inhaled fluticasone furoate/vilanterol (4 times the recommended dose of vilanterol, representing a 12- or 10-fold higher systemic exposure than seen in patients with COPD or asthma, respectively) have been associated with clinically significant prolongation of the QTc interval, which has the potential for producing ventricular arrhythmias. Therefore, BREO ELLIPTA, like other sympathomimetic amines, should be used with caution in patients with cardiovascular disorders, especially coronary insufficiency, cardiac arrhythmias, and hypertension.

In a mortality trial with a median treatment duration of 1.5 years in 16,568 patients with moderate COPD and cardiovascular disease, the annualized incidence rate of adjudicated cardiovascular events (composite of myocardial infarction, stroke, unstable angina, transient ischemic attack, or on-treatment death due to cardiovascular events) was 2.5 per 100 patient-years for BREO ELLIPTA 100/25 mcg, 2.7 for placebo, 2.4 for fluticasone furoate 100 mcg, and 2.6 for vilanterol 25 mcg. Adjudicated, on-treatment deaths due to cardiovascular events occurred in 82 patients receiving BREO ELLIPTA 100/25 mcg, 86 patients receiving placebo, 80 patients receiving fluticasone furoate 100 mcg, and 90 patients receiving vilanterol 25 mcg (annualized incidence rate ranged from 1.2 to 1.3 per 100 patient-years for the treatment groups).

5.13 Reduction in Bone Mineral Density

Decreases in bone mineral density (BMD) have been observed with long-term administration of products containing ICS. The clinical significance of small changes in BMD with regard to long-term consequences such as fracture is unknown. Patients with major risk factors for decreased bone mineral content, such as prolonged immobilization, family history of osteoporosis, postmenopausal status, tobacco use, advanced age, poor nutrition, or chronic use of drugs that can reduce bone mass (e.g., anticonvulsants, oral corticosteroids) should be monitored and treated with established standards of care. Since patients with COPD often have multiple risk factors for reduced BMD, assessment of BMD is recommended prior to initiating BREO ELLIPTA and periodically thereafter. If significant reductions in BMD are seen and BREO ELLIPTA is still considered medically important for that patient’s COPD therapy, use of therapy to treat or prevent osteoporosis should be strongly considered.

In replicate 12-month trials in 3,255 patients with moderate to severe COPD, bone fractures were reported by 2% of patients receiving the fluticasone furoate/vilanterol combination (50/25 mcg: 2% [14 of 820 patients]; 100/25 mcg: 2% [19 of 806 patients]; or 200/25 mcg: 2% [14 of 811 patients]) compared with <1% of patients receiving vilanterol 25 mcg alone (8 of 818 patients).

Similar findings were seen in a mortality trial with a median treatment duration of 1.5 years in 16,568 patients with moderate COPD and cardiovascular disease.

5.14 Effect on Growth

Orally inhaled corticosteroids, , including fluticasone furoate, a component in BREO ELLIPTA may cause a reduction in growth velocity when administered to pediatric patients. The safety and effectiveness of BREO ELLIPTA have not been established in pediatric patients less than 5 years of age. Monitor the growth of pediatric patients receiving BREO ELLIPTA routinely (e.g., via stadiometry). To minimize the systemic effects of orally inhaled corticosteroids, including BREO ELLIPTA, titrate each patient’s dose to the lowest dosage that effectively controls his/her symptoms [see Dosage and Administration (2.3), Use in Specific Populations (8.4)].

5.15 Glaucoma and Cataracts

Glaucoma, increased intraocular pressure, and cataracts have been reported in patients with COPD or asthma following the long-term administration of ICS, including fluticasone furoate, a component in BREO ELLIPTA. Consider referral to an ophthalmologist in patients who develop ocular symptoms or use BREO ELLIPTA long term.

5.16 Risk of Using Sympathomimetic Amines in Certain Coexisting Conditions

BREO ELLIPTA, like all therapies containing sympathomimetic amines, should be used with caution in patients with convulsive disorders, thyrotoxicosis, or diabetes mellitus and in those who are unusually responsive to sympathomimetic amines. Doses of the related beta2-adrenoceptor agonist albuterol, when administered intravenously, have been reported to aggravate preexisting diabetes mellitus and ketoacidosis.

5.17 Hyperglycemia and Hypokalemia

There have been reports of increases in blood glucose levels with BREO ELLIPTA. This should be considered in patients with a history of, or with risk factors for, diabetes mellitus [see Adverse Reactions (6.3)].

Beta-adrenergic agonist therapies may produce significant hypokalemia in some patients, possibly through intracellular shunting, which has the potential to produce adverse cardiovascular effects. The decrease in serum potassium is usually transient, not requiring supplementation. In clinical trials evaluating BREO ELLIPTA in patients with COPD or asthma, there was no evidence of a treatment effect on serum potassium.

6 ADVERSE REACTIONS

The following clinically significant adverse reactions are described elsewhere in labeling:

- Serious Asthma-Related Events – Hospitalizations, Intubations, Death [see Warnings and Precautions (5.1)]
- Oropharyngeal Candidiasis [see Warnings and Precautions (5.4)]
- Pneumonia [see Warnings and Precautions (5.5)]
- Immunosuppression and Risk of Infections [see Warnings and Precautions (5.6)]
- Hypercorticism and Adrenal Suppression [see Warnings and Precautions (5.8)]
- Paradoxical Bronchospasm [see Warnings and Precautions (5.10)]
- Cardiovascular Effects [see Warnings and Precautions (5.12)]
- Reduction in Bone Mineral Density [see Warnings and Precautions (5.13)]
- Growth Effects [see Warnings and Precautions (5.14)]
- Glaucoma and Cataracts [see Warnings and Precautions (5.15)]

Because clinical trials are conducted under widely varying conditions, adverse reaction rates observed in the clinical trials of a drug cannot be directly compared with rates in the clinical trials of another drug and may not reflect the rates observed in practice.

6.1 Clinical Trials Experience in Chronic Obstructive Pulmonary Disease

The safety data described below are based on two 6-month and two 12-month trials and one long-term mortality trial. In these studies, 5,356 patients with COPD received at least 1 dose of BREO ELLIPTA 100/25 mcg. Adverse reactions observed in other studies of BREO ELLIPTA in COPD patients were similar to those observed in these 5 trials.

6-Month Trials

The incidence of adverse reactions associated with BREO ELLIPTA 100/25 mcg in Table 2 is based on 2 placebo-controlled, 6-month clinical trials (Trials 1 and 2; n = 1,224 and n = 1,030, respectively). Of the 2,254 patients, 70% were male and 84% were White. They had a mean age of 62 years and an average smoking history of 44 pack years, with 54% identified as current smokers. At screening, the mean postbronchodilator percent predicted FEV1 was 48% (range: 14% to 87%), the mean postbronchodilator FEV1/forced vital capacity (FVC) ratio was 47% (range: 17% to 88%), and the mean percent reversibility was 14% (range: -41% to 152%).

Patients received 1 inhalation once daily of the following: BREO ELLIPTA 100/25 mcg, BREO ELLIPTA 200/25 mcg, fluticasone furoate/vilanterol 50/25 mcg, fluticasone furoate 100 mcg, fluticasone furoate 200 mcg, vilanterol 25 mcg, or placebo.

Table 2. Adverse Reactions with BREO ELLIPTA 100/25 mcg with ≥3% Incidence and More Common than Placebo in Patients with Chronic Obstructive Pulmonary Disease
Adverse Reaction | BREO ELLIPTA; 100/25 mcg; (n = 410); % | Vilanterol; 25 mcg; (n = 408); % | Fluticasone Furoate; 100 mcg; (n = 410); % | Placebo; (n = 412); %
Infections and infestations
Nasopharyngitis | 9 | 10 | 8 | 8
Upper respiratory tract infection | 7 | 5 | 4 | 3
Oropharyngeal candidiasisa | 5 | 2 | 3 | 2
Nervous system disorders
Headache | 7 | 9 | 7 | 5
a Includes oral candidiasis, oropharyngeal candidiasis, candidiasis, and fungal oropharyngitis.

12-Month Trials

Long-term safety data are based on two 12-month trials (Trials 3 and 4; n = 1,633 and n = 1,622, respectively). Trials 3 and 4 included 3,255 patients, of which 57% were male and 85% were White. They had a mean age of 64 years and an average smoking history of 46 pack years, with 44% identified as current smokers. At screening, the mean postbronchodilator percent predicted FEV1 was 45% (range: 12% to 91%), and the mean postbronchodilator FEV1/FVC ratio was 46% (range: 17% to 81%), indicating that the patient population had moderate to very severely impaired airflow obstruction. Patients received 1 inhalation once daily of the following: BREO ELLIPTA 100/25 mcg, BREO ELLIPTA 200/25 mcg, fluticasone furoate/vilanterol 50/25 mcg, or vilanterol 25 mcg. In addition to the reactions shown in Table 2, adverse reactions occurring in ≥3% of the patients treated with BREO ELLIPTA 100/25 mcg (n = 806) for 12 months included back pain, pneumonia [see Warnings and Precautions (5.5)], bronchitis, sinusitis, cough, oropharyngeal pain, arthralgia, influenza, pharyngitis, and pyrexia.

Mortality Trial

Safety data are available from a mortality trial in patients with moderate COPD (moderate airflow limitation [≥50% and ≤70% predicted FEV1]) who either had a history of, or were at risk of, cardiovascular disease and were treated for up to 4 years (median treatment duration of 1.5 years). The trial included 16,568 patients, 4,140 of whom received BREO ELLIPTA 100/25 mcg. In addition to the events in COPD trials shown in Table 2, adverse reactions occurring in ≥3% of the patients treated with BREO ELLIPTA 100/25 mcg and more common than placebo included pneumonia, back pain, hypertension, and influenza.

6.2 Clinical Trials Experience in Asthma

The safety data described below were based on trials that evaluated BREO ELLIPTA 100/25 mcg in 1,757 patients and BREO ELLIPTA 200/25 mcg in 745 patients. While patients aged 12 to 17 years were included in these trials, BREO ELLIPTA 200/25 mcg is not approved for use in this age group [see Dosage and Administration (2.2)].

One additional 24-week trial enrolled 902 pediatric patients with asthma. In this trial, BREO ELLIPTA 100/25 mcg was studied in 117 patients aged 12 to 17 years and BREO ELLIPTA 50/25 mcg was studied in 337 patients aged 5 to 11 years.

Adult Patients

The safety of BREO ELLIPTA for the maintenance treatment of asthma in adult patients was based on the data from Trials 8, 9, 10, 11, and 12 [see Clinical Studies (14.2)]. Trial 8 was a 12-week trial that evaluated the efficacy of BREO ELLIPTA 100/25 mcg in patients with asthma compared with fluticasone furoate 100 mcg and placebo. The incidence of adverse reactions associated with BREO ELLIPTA 100/25 mcg is shown in Table 3.

Table 3. Adverse Reactions with BREO ELLIPTA 100/25 mcg with ≥2% Incidence and More Common than Placebo in Patients with Asthma (Trial 8)
Adverse Reaction | BREO ELLIPTA; 100/25 mcg; (n = 201); % | Fluticasone Furoate; 100 mcg; (n = 205); % | Placebo; (n = 203); %
Infections and infestations
Nasopharyngitis | 10 | 7 | 7
Oral candidiasisa | 2 | 2 | 0
Nervous system disorders
Headache | 5 | 4 | 4
Respiratory, thoracic, and mediastinal disorders
Oropharyngeal pain | 2 | 2 | 1
Dysphonia | 2 | 1 | 0
a Includes oral candidiasis and oropharyngeal candidiasis.

Trial 9 was a 12-week trial that evaluated the efficacy of BREO ELLIPTA 100/25 mcg, BREO ELLIPTA 200/25 mcg, and fluticasone furoate 100 mcg in patients with asthma. This trial did not have a placebo arm. The incidence of adverse reactions associated with BREO ELLIPTA 100/25 mcg and BREO ELLIPTA 200/25 mcg is shown in Table 4.

Table 4. Adverse Reactions with BREO ELLIPTA 100/25 mcg and BREO ELLIPTA 200/25 mcg with ≥2% Incidence in Patients with Asthma (Trial 9)
Adverse Reaction | BREO ELLIPTA; 200/25 mcg; (n = 346); % | BREO ELLIPTA; 100/25 mcg; (n = 346); % | Fluticasone Furoate; 100 mcg; (n = 347); %
Nervous system disorders
Headache | 8 | 8 | 9
Infections and infestations
Nasopharyngitis | 7 | 6 | 7
Influenza | 3 | 3 | 1
Upper respiratory tract infection | 2 | 2 | 3
Sinusitis | 2 | 1 | <1
Bronchitis | 2 | <1 | 2
Respiratory, thoracic, and mediastinal disorders
Oropharyngeal pain | 2 | 2 | 1
Cough | 1 | 2 | 1

24-Week Trial

Trial 10 was a 24-week trial that evaluated the efficacy of BREO ELLIPTA 200/25 mcg once daily, fluticasone furoate 200 mcg once daily, and fluticasone propionate 500 mcg twice daily in patients with asthma. This trial did not have a placebo arm. In addition to the reactions shown in Tables 3 and 4, adverse reactions occurring in ≥2% of patients treated with BREO ELLIPTA 200/25 mcg included viral respiratory tract infection, pharyngitis, pyrexia, and arthralgia.

12-Month Trial

Long-term safety data are based on a 12-month trial that evaluated the safety of BREO ELLIPTA 100/25 mcg once daily (n = 201), BREO ELLIPTA 200/25 mcg once daily (n = 202), and fluticasone propionate 500 mcg twice daily (n = 100) in patients with asthma (Trial 11). In addition to the reactions shown in Tables 3 and 4, adverse reactions occurring in ≥2% of the patients treated with BREO ELLIPTA 100/25 mcg or BREO ELLIPTA 200/25 mcg for 12 months included pyrexia, back pain, extrasystoles, upper abdominal pain, respiratory tract infection, allergic rhinitis, pharyngitis, rhinitis, arthralgia, supraventricular extrasystoles, ventricular extrasystoles, acute sinusitis, and pneumonia.

Adult and Pediatric Patients Aged 12 to 17 Years Exacerbation Trial

Trial 12 included both adult and pediatric patients 12 years of age and older. Although this trial did not support efficacy of BREO ELLIPTA for maintenance treatment of asthma in pediatric patients 12 to 17 years of age, it was used to evaluate safety in both adult and pediatric patients 12 to 17 years of age. Patients received BREO ELLIPTA 100/25 mcg (n = 1,009) or fluticasone furoate 100 mcg (n = 1,010). Patients participating in this trial had a history of 1 or more asthma exacerbations that required treatment with oral/systemic corticosteroids or emergency department visit or in-patient hospitalization for the treatment of asthma in the year prior to trial entry. Asthma-related hospitalizations occurred in 10 patients (1%) treated with BREO ELLIPTA 100/25 mcg compared with 7 patients (0.7%) treated with fluticasone furoate 100 mcg. Among patients aged 12 to 17 years, asthma-related hospitalizations occurred in 4 patients (2.6%) treated with BREO ELLIPTA 100/25 mcg (n = 151) compared with 0 patients treated with fluticasone furoate 100 mcg (n = 130). There were no asthma-related deaths or asthma-related intubations observed in this trial.

Pediatric Patients Aged 5 to 17 Years

The safety of BREO ELLIPTA for the maintenance treatment of asthma in pediatric patients 5 years and older was based on the data from Trial 14, a 24-week clinical trial that enrolled 902 patients with asthma aged 5 to 17 years (aged 5 to 11 years [n = 673]; aged 12 to 17 years [n = 229]). Pediatric patients aged 12 to 17 years were randomized to BREO ELLIPTA 100/25 mcg (n = 117) or fluticasone furoate 100 mcg (n = 112). Pediatric patients aged 5 to 11 years were randomized to BREO ELLIPTA 50/25 mcg (n = 337) or fluticasone furoate 50 mcg (n = 336) [see Clinical Studies (14.2)]. Adverse reactions reported in ≥3% of pediatric patients treated with BREO ELLIPTA is shown in Table 5.

Table 5. Adverse Reactions with BREO ELLIPTA with ≥3% Incidence in Pediatric Patients with Asthma (Trial 14)
Adverse Reaction | BREO ELLIPTAa; (n = 454); % | Fluticasone Furoateb; (n = 448); %
Infections and infestations
Nasopharyngitis | 10 | 8
Upper respiratory tract infection | 7 | 6
Rhinitis | 3 | 1
Viral upper respiratory tract infection | 3 | <1
Respiratory, thoracic, and mediastinal disorders
Rhinitis allergic | 4 | 1
Nervous system disorders
Headache | 3 | 2
a The dose of BREO ELLIPTA was 100/25 mcg once daily for pediatric patients aged 12 to 17 years and 50/25 mcg once daily for pediatric patients aged 5 to 11 years.
b The dose of fluticasone furoate was 100 mcg once daily for pediatric patients aged 12 to 17 years and 50 mcg once daily for pediatric patients aged 5 to 11 years.

6.3 Postmarketing Experience

In addition to adverse reactions reported from clinical trials, the following adverse reactions have been identified during post approval use of BREO ELLIPTA. Because these reactions are reported voluntarily from a population of uncertain size, it is not always possible to reliably estimate their frequency or establish a causal relationship to drug exposure. These events have been chosen for inclusion due to either their seriousness, frequency of reporting, or causal connection to BREO ELLIPTA or a combination of these factors.

Cardiac Disorders

Palpitations, tachycardia.

Immune System Disorders

Hypersensitivity reactions, including anaphylaxis, angioedema, rash, and urticaria.

Metabolism and Nutrition Disorders

Hyperglycemia.

Musculoskeletal and Connective Tissue Disorders

Muscle spasms.

Nervous System Disorders

Tremor.

Psychiatric Disorders

Nervousness.

Respiratory, Thoracic, and Mediastinal Disorders

Paradoxical bronchospasm.

7 DRUG INTERACTIONS

7.1 Inhibitors of Cytochrome P450 3A4

Fluticasone furoate and vilanterol are both substrates of CYP3A4. Concomitant administration of the strong CYP3A4 inhibitor ketoconazole increases the systemic exposure to fluticasone furoate and vilanterol. Caution should be exercised when considering the coadministration of BREO ELLIPTA with ketoconazole and other known strong CYP3A4 inhibitors [see Warnings and Precautions (5.9), Clinical Pharmacology (12.3)].

7.2 Monoamine Oxidase Inhibitors, Tricyclic Antidepressants, and QTc Prolonging Drugs

Vilanterol, like other beta2-agonists, should be administered with extreme caution to patients being treated with monoamine oxidase inhibitors, tricyclic antidepressants, or drugs known to prolong the QTc interval or within 2 weeks of discontinuation of such agents, because the effect of adrenergic agonists on the cardiovascular system may be potentiated by these agents. Drugs that are known to prolong the QTc interval have an increased risk of ventricular arrhythmias.

7.3 Beta-Adrenergic Receptor Blocking Agents

Beta-blockers not only block the pulmonary effect of beta-agonists, such as vilanterol, but may also produce severe bronchospasm in patients with COPD or asthma. Therefore, patients with COPD or asthma should not normally be treated with beta-blockers. However, under certain circumstances, there may be no acceptable alternatives to the use of beta-adrenergic blocking agents for these patients; cardioselective beta-blockers could be considered, although they should be administered with caution.

7.4 Non–Potassium-Sparing Diuretics

The electrocardiographic changes and/or hypokalemia that may result from the administration of non–potassium-sparing diuretics (such as loop or thiazide diuretics) can be acutely worsened by beta-agonists, especially when the recommended dose of the beta-agonist is exceeded. Although the clinical significance of these effects is not known, caution is advised in the coadministration of beta-agonists with non–potassium-sparing diuretics.

8 USE IN SPECIFIC POPULATIONS

8.1 Pregnancy

Risk Summary

There are insufficient data on the use of BREO ELLIPTA or its individual components, fluticasone furoate and vilanterol, in pregnant women to inform a drug-associated risk. (See Clinical Considerations.) In an animal reproduction study, fluticasone furoate and vilanterol administered by inhalation alone or in combination to pregnant rats during the period of organogenesis produced no fetal structural abnormalities. The highest fluticasone furoate and vilanterol doses in this study were approximately 5 and 40 times the maximum recommended human daily inhalation doses (MRHDID) of 200 and 25 mcg, respectively. (See Data.)

The estimated risk of major birth defects and miscarriage for the indicated populations is unknown. In the U.S. general population, the estimated risk of major birth defects and miscarriage in clinically recognized pregnancies is 2% to 4% and 15% to 20%, respectively.

Clinical Considerations

Disease-Associated Maternal and/or Embryofetal Risk: In women with poorly or moderately controlled asthma, there is an increased risk of several perinatal outcomes such as pre-eclampsia in the mother and prematurity, low birth weight, and small for gestational age in the neonate. Pregnant women should be closely monitored, and medication adjusted as necessary to maintain optimal control of asthma.

Labor or Delivery: BREO ELLIPTA should be used during late gestation and labor only if the potential benefit justifies the potential for risks related to beta-agonists interfering with uterine contractility.

Data

Animal Data: Fluticasone Furoate and Vilanterol: In an embryofetal developmental study, pregnant rats received fluticasone furoate and vilanterol during the period of organogenesis at doses up to approximately 5 and 40 times the MRHDID of 200 and 25 mcg, respectively, alone or in combination (on a mcg/m^2 basis at inhalation doses up to approximately 95 mcg/kg/day). No evidence of structural abnormalities was observed.

Fluticasone Furoate: In 2 separate embryofetal developmental studies, pregnant rats and rabbits received fluticasone furoate during the period of organogenesis at doses up to approximately 4 and 1 times, respectively, the MRHDID of 200 mcg (on a mcg/m^2 basis at maternal inhalation doses up to 91 and 8 mcg/kg/day, respectively). No evidence of structural abnormalities in fetuses was observed in either species. In a perinatal and postnatal developmental study in rats, dams received fluticasone furoate during late gestation and lactation periods at doses up to approximately 1 time the MRHDID of 200 mcg (on a mcg/m^2 basis at maternal inhalation doses up to 27 mcg/kg/day). No evidence of effects on offspring development was observed.

Vilanterol: In 2 separate embryofetal developmental studies, pregnant rats and rabbits received vilanterol during the period of organogenesis at doses up to approximately 13,000 and 1,000 times, respectively, the MRHDID (on a mcg/m^2 basis at maternal inhalation doses up to 33,700 mcg/kg/day in rats and on an AUC basis at maternal inhaled doses up to 5,740 mcg/kg/day in rabbits). No evidence of structural abnormalities was observed at any dose in rats or in rabbits up to approximately 160 times the MRHDID (on an AUC basis at maternal doses up to 591 mcg/kg/day). However, fetal skeletal variations were observed in rabbits at approximately 1,000 times the MRHDID (on an AUC basis at maternal inhaled or subcutaneous doses of 5,740 or 300 mcg/kg/day, respectively). The skeletal variations included decreased or absent ossification in cervical vertebral centrum and metacarpals. In a perinatal and postnatal developmental study in rats, dams received vilanterol during late gestation and the lactation periods at doses up to approximately 3,900 times the MRHDID (on a mcg/m^2 basis at maternal oral doses up to 10,000 mcg/kg/day). No evidence of effects in offspring development was observed.

8.2 Lactation

Risk Summary

There is no information available on the presence of fluticasone furoate or vilanterol in human milk, the effects on the breastfed child, or the effects on milk production. Low concentrations of other ICS have been detected in human milk. The developmental and health benefits of breastfeeding should be considered along with the mother’s clinical need for BREO ELLIPTA and any potential adverse effects on the breastfed child from fluticasone furoate or vilanterol or from the underlying maternal condition.

8.4 Pediatric Use

The safety and effectiveness of BREO ELLIPTA for the maintenance treatment of asthma in pediatric patients 5 years of age and older have been established. This indication is based on Trial 14, an adequate and well-controlled trial in pediatric patients aged 5 to 17 years [see Adverse Reactions (6.2), Clinical Studies (14.2)]. The recommended dosage for pediatric patients is different than the adult dosage [see Dosage and Administration (2.2)].

The safety and efficacy of BREO ELLIPTA in pediatric patients aged younger than 5 years have not been established.

In Trial 12, an exacerbation trial [see Clinical Studies (14.2)], pediatric patients aged 12 to 17 years (n = 281) were treated with BREO ELLIPTA 100/25 mcg (n = 151) or treated with fluticasone furoate 100 mcg (n = 130). Among these patients, 10% of patients treated with BREO ELLIPTA 100/25 mcg reported an asthma exacerbation compared with 7% for patients treated with fluticasone furoate 100 mcg. Asthma-related hospitalizations occurred in 4 patients (2.6%) treated with BREO ELLIPTA 100/25 mcg compared with 0 patients treated with fluticasone furoate 100 mcg.

Effects on Growth

Orally inhaled corticosteroids may cause a reduction in growth velocity when administered to pediatric patients. A reduction of growth velocity in pediatric patients may occur as a result of poorly controlled asthma or from use of corticosteroids, including ICS. The effects of long-term treatment of pediatric patients with ICS, including fluticasone furoate, on final adult height are not known.

Controlled clinical trials have shown that ICS may cause a reduction in growth in children. In these trials, the mean reduction in growth velocity was approximately 1 cm/year (range: 0.3 to 1.8 cm/year) and appears to be related to dose and duration of exposure. This effect has been observed in the absence of laboratory evidence of HPA axis suppression, suggesting that growth velocity is a more sensitive indicator of systemic corticosteroid exposure in children than some commonly used tests of HPA axis function. The long-term effects of this reduction in growth velocity associated with orally inhaled corticosteroids, including the impact on final adult height, are unknown. The potential for “catch-up” growth following discontinuation of treatment with orally inhaled corticosteroids has not been adequately studied. The growth of pediatric patients receiving orally inhaled corticosteroids, including BREO ELLIPTA, should be monitored routinely (e.g., via stadiometry). The potential growth effects of prolonged treatment should be weighed against the clinical benefits obtained and the risks associated with alternative therapies. To minimize the systemic effects of orally inhaled corticosteroids, including BREO ELLIPTA, each patient should be titrated to the lowest dose that effectively controls his/her symptoms.

A randomized, double-blind, parallel-group, multicenter, 1-year, placebo-controlled trial evaluated the effect of once-daily treatment with orally inhaled fluticasone furoate 50 mcg on growth velocity assessed by stadiometry. The patients were 457 prepubertal children (girls aged 5 to <8 years and boys aged 5 to <9 years). Mean growth velocity over the 52-week treatment period was lower in the patients receiving orally inhaled fluticasone furoate (5.905 cm/year) compared with placebo (6.065 cm/year). The mean reduction in growth velocity was 0.16 cm/year (95% CI: -0.14, 0.46) [see Warnings and Precautions (5.14)].

8.5 Geriatric Use

Based on available data, no adjustment of the dosage of BREO ELLIPTA in geriatric patients is necessary, but greater sensitivity in some older individuals cannot be ruled out.

Clinical trials of BREO ELLIPTA for COPD included 4,820 subjects aged 65 years and older and 1,118 subjects aged 75 years and older. Clinical trials of BREO ELLIPTA for asthma included 854 subjects aged 65 years and older. No overall differences in safety or effectiveness were observed between these subjects and younger subjects, and other reported clinical experience has not identified differences in responses between the elderly and younger patients.

8.6 Hepatic Impairment

Fluticasone furoate systemic exposure increased by up to 3-fold in adult patients with hepatic impairment compared with healthy subjects. Hepatic impairment had no effect on vilanterol systemic exposure. Use BREO ELLIPTA with caution in patients with moderate or severe hepatic impairment. Monitor patients for corticosteroid-related side effects. The effect of hepatic impairment on fluticasone furoate and vilanterol systemic exposure in patients aged younger than 18 years has not been evaluated [see Clinical Pharmacology (12.3)].

8.7 Renal Impairment

There were no significant increases in either fluticasone furoate or vilanterol exposure in patients with severe renal impairment (CrCl <30 mL/min) compared with healthy subjects. No dosage adjustment is required in patients with renal impairment [see Clinical Pharmacology (12.3)].

10 OVERDOSAGE

BREO ELLIPTA contains both fluticasone furoate and vilanterol; therefore, the risks associated with overdosage for the individual components described below apply to BREO ELLIPTA. Treatment of overdosage consists of discontinuation of BREO ELLIPTA together with institution of appropriate symptomatic and/or supportive therapy. The judicious use of a cardioselective beta-receptor blocker may be considered, bearing in mind that such medicine can produce bronchospasm. Cardiac monitoring is recommended in cases of overdosage.

Fluticasone Furoate

Because of low systemic bioavailability (15.2%) and an absence of acute drug-related systemic findings in clinical trials, overdosage of fluticasone furoate is unlikely to require any treatment other than observation. If used at excessive doses for prolonged periods, systemic effects such as hypercorticism may occur [see Warnings and Precautions (5.8)].

Vilanterol

The expected signs and symptoms with overdosage of vilanterol are those of excessive beta-adrenergic stimulation and/or occurrence or exaggeration of any of the signs and symptoms of beta-adrenergic stimulation (e.g., seizures, angina, hypertension or hypotension, tachycardia with rates up to 200 beats/min, arrhythmias, nervousness, headache, tremor, muscle cramps, dry mouth, palpitation, nausea, dizziness, fatigue, malaise, insomnia, hyperglycemia, hypokalemia, metabolic acidosis). As with all inhaled sympathomimetic medicines, cardiac arrest and even death may be associated with an overdose of vilanterol.

11 DESCRIPTION

BREO ELLIPTA is an inhalation powder drug product for delivery of a combination of fluticasone furoate (an ICS) and vilanterol (a LABA) to patients by oral inhalation.

Fluticasone furoate, a synthetic trifluorinated corticosteroid, has the chemical name (6α,11β,16α,17α)-6,9-difluoro-17-{[(fluoro-methyl)thio]carbonyl}-11-hydroxy-16-methyl-3-oxoandrosta-1,4-dien-17-yl 2-furancarboxylate and the following chemical structure:

Fluticasone furoate is a white powder with a molecular weight of 538.6, and the empirical formula is C27H29F3O6S. It is practically insoluble in water.

Vilanterol trifenatate has the chemical name triphenylacetic acid-4-{(1R)-2-[(6-{2-[2,6-dicholorobenzyl)oxy]ethoxy}hexyl)amino]-1-hydroxyethyl}-2-(hydroxymethyl)phenol (1:1) and the following chemical structure:

Vilanterol trifenatate is a white powder with a molecular weight of 774.8, and the empirical formula is C24H33Cl2NO5•C20H16O2. It is practically insoluble in water.

BREO ELLIPTA is a light grey and pale blue plastic inhaler containing 2 foil blister strips. Each blister on one strip contains a white powder blend of micronized fluticasone furoate (50, 100, or 200 mcg) and lactose monohydrate (12.5, 12.4 or 12.3 mg, respectively), and each blister on the other strip contains a white powder blend of micronized vilanterol trifenatate (40 mcg equivalent to 25 mcg of vilanterol), magnesium stearate (125 mcg), and lactose monohydrate (12.34 mg). The lactose monohydrate contains milk proteins. After the inhaler is activated, the powder within both blisters is exposed and ready for dispersion into the airstream created by the patient inhaling through the mouthpiece.

Under standardized in vitro test conditions, BREO ELLIPTA delivers 46, 92 or 184 mcg of fluticasone furoate and 22 mcg of vilanterol per dose when tested at a flow rate of 60 L/min for 4 seconds.

In adult patients with obstructive lung disease and severely compromised lung function (COPD with FEV1/FVC <70% and FEV1 <30% predicted or FEV1 <50% predicted plus chronic respiratory failure), mean peak inspiratory flow through the ELLIPTA inhaler was 66.5 L/min (range: 43.5 to 81.0 L/min).

In adult patients with severe asthma, mean peak inspiratory flow through the ELLIPTA inhaler was 96.6 L/min (range: 72.4 to 124.6 L/min). In pediatric patients with asthma aged 5 to 11 years, mean peak inspiratory flow through the ELLIPTA inhaler was 60.6 L/min (range: 36.3 to 82.5 L/min).

The actual amount of drug delivered to the lung will depend on patient factors, such as inspiratory flow profile.

12 CLINICAL PHARMACOLOGY

12.1 Mechanism of Action

BREO ELLIPTA

BREO ELLIPTA contains both fluticasone furoate and vilanterol. The mechanisms of action described below for the individual components apply to BREO ELLIPTA. These drugs represent 2 different classes of medications (an ICS and a LABA), each having different effects on clinical and physiological indices.

Fluticasone Furoate

Fluticasone furoate is a synthetic trifluorinated corticosteroid with anti-inflammatory activity. Fluticasone furoate has been shown in vitro to exhibit a binding affinity for the human glucocorticoid receptor that is approximately 29.9 times that of dexamethasone and 1.7 times that of fluticasone propionate. The clinical relevance of these findings is unknown.

The precise mechanism through which fluticasone furoate affects COPD and asthma symptoms is not known. Inflammation is an important component in the pathogenesis of COPD and asthma. Corticosteroids have been shown to have a wide range of actions on multiple cell types (e.g., mast cells, eosinophils, neutrophils, macrophages, lymphocytes) and mediators (e.g., histamine, eicosanoids, leukotrienes, cytokines) involved in inflammation. Specific effects of fluticasone furoate demonstrated in in vitro and in vivo models included activation of the glucocorticoid response element, inhibition of pro-inflammatory transcription factors such as NFkB, and inhibition of antigen-induced lung eosinophilia in sensitized rats. These anti-inflammatory actions of corticosteroids may contribute to their efficacy.

Vilanterol

Vilanterol is a LABA. In vitro tests have shown the functional selectivity of vilanterol was similar to salmeterol. The clinical relevance of this in vitro finding is unknown.

Although beta2-receptors are the predominant adrenergic receptors in bronchial smooth muscle and beta1-receptors are the predominant receptors in the heart, there are also beta2-receptors in the human heart comprising 10% to 50% of the total beta-adrenergic receptors. The precise function of these receptors has not been established, but they raise the possibility that even highly selective beta2-agonists may have cardiac effects.

The pharmacologic effects of beta2-adrenergic agonist drugs, including vilanterol, are at least in part attributable to stimulation of intracellular adenyl cyclase, the enzyme that catalyzes the conversion of adenosine triphosphate (ATP) to cyclic-3′,5′-adenosine monophosphate (cyclic AMP). Increased cyclic AMP levels cause relaxation of bronchial smooth muscle and inhibition of release of mediators of immediate hypersensitivity from cells, especially from mast cells.

12.2 Pharmacodynamics

Cardiac Electrophysiology

Healthy Subjects: QTc interval prolongation was studied in a double-blind, multiple-dose, placebo- and positive-controlled crossover study in 85 healthy volunteers. The maximum mean (95% upper confidence bound) difference in QTcF from placebo after baseline correction was 4.9 (7.5) milliseconds and 9.6 (12.2) milliseconds seen 30 minutes after dosing for fluticasone furoate/vilanterol 200/25 mcg and fluticasone furoate/vilanterol 800/100 mcg, respectively.

A dose-dependent increase in heart rate was also observed. The maximum mean (95% upper confidence bound) difference in heart rate from placebo after baseline-correction was 7.8 (9.4) beats/min and 17.1 (18.7) beats/min seen 10 minutes after dosing for fluticasone furoate/vilanterol 200/25 mcg and fluticasone furoate/vilanterol 800/100 mcg, respectively.

Hypothalamic-Pituitary-Adrenal Axis Effects

Healthy Subjects: Inhaled fluticasone furoate at repeat doses up to 400 mcg was not associated with statistically significant decreases in serum or urinary cortisol in healthy subjects. Decreases in serum and urine cortisol levels were observed at fluticasone furoate exposures several-fold higher than exposures observed at the therapeutic dose.

Patients with Chronic Obstructive Pulmonary Disease: In a trial with patients with COPD, treatment with fluticasone furoate (50, 100, or 200 mcg)/vilanterol 25 mcg, vilanterol 25 mcg, or fluticasone furoate (100 or 200 mcg) for 6 months did not affect 24-hour urinary cortisol excretion. A separate trial with patients with COPD demonstrated no effects on serum cortisol after 28 days of treatment with fluticasone furoate (50, 100, or 200 mcg)/vilanterol 25 mcg.

Patients with Asthma: A randomized, double-blind, parallel-group trial in 104 pediatric patients with asthma (aged 5 to 11 years) showed no difference between once-daily treatment with inhaled fluticasone furoate 50 mcg compared with placebo on serum cortisol weighted mean (0 to 24 hours) and serum cortisol AUC(0-24) following 6 weeks of treatment.

A randomized, double-blind, parallel-group trial in 185 patients with asthma aged 12 to 65 years showed no difference between once-daily treatment with fluticasone furoate/vilanterol 100/25 mcg or fluticasone furoate/vilanterol 200/25 mcg compared with placebo on serum cortisol weighted mean (0 to 24 hours), serum cortisol AUC(0-24), and 24-hour urinary cortisol after 6 weeks of treatment, whereas prednisolone 10 mg given once daily for 7 days resulted in significant cortisol suppression.

12.3 Pharmacokinetics

Linear pharmacokinetics was observed for fluticasone furoate (200 to 800 mcg) and vilanterol (25 to 100 mcg). On repeated once-daily inhalation administration, steady state of fluticasone furoate and vilanterol plasma concentrations was achieved after 6 days, and the accumulation was up to 2.6-fold for fluticasone furoate and 2.4-fold for vilanterol as compared with single dose.

Absorption

Fluticasone Furoate: Fluticasone furoate plasma levels may not predict therapeutic effect. Peak plasma concentrations are reached within 0.5 to 1 hour. Absolute bioavailability of fluticasone furoate when administered by inhalation was 15.2%, primarily due to absorption of the inhaled portion of the dose delivered to the lung. Oral bioavailability from the swallowed portion of the dose is low (approximately 1.3%) due to extensive first-pass metabolism. Systemic exposure (AUC) in patients with COPD or asthma was 46% or 7% lower, respectively, than observed in healthy subjects.

Vilanterol: Vilanterol plasma levels may not predict therapeutic effect. Peak plasma concentrations are reached within 10 minutes following inhalation. Absolute bioavailability of vilanterol when administered by inhalation was 27.3%, primarily due to absorption of the inhaled portion of the dose delivered to the lung. Oral bioavailability from the swallowed portion of the dose of vilanterol is low (<2%) due to extensive first-pass metabolism. Systemic exposure (AUC) in patients with COPD was 24% higher than observed in healthy subjects. Systemic exposure (AUC) in patients with asthma was 21% lower than observed in healthy subjects.

Distribution

Fluticasone Furoate: Following intravenous administration to healthy subjects, the mean volume of distribution at steady state was 661 L. Binding of fluticasone furoate to human plasma proteins was high (>99%).

Vilanterol: Following intravenous administration to healthy subjects, the mean volume of distribution at steady state was 165 L. Binding of vilanterol to human plasma proteins was on average 94%.

Elimination

Metabolism: Fluticasone Furoate: Fluticasone furoate is cleared from systemic circulation principally by hepatic metabolism via CYP3A4 to metabolites with significantly reduced corticosteroid activity. There was no in vivo evidence for cleavage of the furoate moiety resulting in the formation of fluticasone.

Vilanterol: Vilanterol is mainly metabolized, principally via CYP3A4, to a range of metabolites with significantly reduced β1- and β2-agonist activity.

Excretion: Fluticasone Furoate: Fluticasone furoate and its metabolites are eliminated primarily in the feces, accounting for approximately 101% and 90% of the orally and intravenously administered doses, respectively. Urinary excretion accounted for approximately 1% and 2% of the orally and intravenously administered doses, respectively. Following repeat-dose inhaled administration, the plasma elimination phase half-life averaged 24 hours.

Vilanterol: Following oral administration, vilanterol was eliminated mainly by metabolism followed by excretion of metabolites in urine and feces (approximately 70% and 30%, respectively, of the recovered radioactive dose). The plasma elimination half-life of vilanterol, as determined from inhalation administration of multiple doses of vilanterol 25 mcg, is 21.3 hours in patients with COPD and 16.0 hours in patients with asthma.

Specific Populations

The effects of renal and hepatic impairment and other intrinsic factors on the pharmacokinetics of fluticasone furoate and vilanterol are shown in Figure 1.

Figure 1. Impact of Intrinsic Factors on the Pharmacokinetics (PK) of Fluticasone Furoate (FF) and Vilanterol (VI) Following Administration as Fluticasone Furoate/Vilanterol Combination

aSevere renal impairment (CrCl <30 mL/min) compared with healthy subjects; mild (Child‑Pugh A), moderate (Child-Pugh B), and severe (Child-Pugh C) hepatic impairment compared with healthy subjects.
bFor COPD and asthma, the following comparisons were made: age compared with ≤65 years, gender compared with female, and ethnicity compared with White.

Pediatric Patients: Fluticasone Furoate: A population pharmacokinetics analysis to assess impact of age on fluticasone furoate systemic exposure was conducted using combined data from clinical trials in pediatric patients aged 5 to 11 years (n = 306). There was no relevant effect of age on the apparent clearance of fluticasone furoate. The dose-adjusted fluticasone furoate systemic exposure at steady state in children aged 5 to 11 years following 50 mcg were comparable to that observed in adult and pediatric patients 12 years and older following dosing with fluticasone furoate 100 mcg monotherapy.

Vilanterol: A population pharmacokinetic analysis was conducted to characterize vilanterol pharmacokinetics using combined data from clinical trials in pediatric patients aged 5 to 11 years (n = 142). There was no relevant effect of age, weight, body mass index, sex, ethnicity, and race on vilanterol clearance. A cross-study comparison in pediatric patients with asthma showed that at steady-state, when combined with fluticasone furoate, vilanterol had similar AUC values but lower Cmax values compared to vilanterol administered alone. Vilanterol systemic exposure at steady state, in patients with asthma aged 5 to 11 years, was similar to those observed in adult and pediatric patients 12 years and older with asthma following repeat dosing of BREO ELLIPTA 100/25 mcg.

Racial or Ethnic Groups: Fluticasone Furoate: Systemic exposure [AUC(0-24)] to inhaled fluticasone furoate 200 mcg was 27% to 49% higher in healthy subjects of Japanese, Korean, and Chinese heritage compared with White subjects. Similar differences were observed for patients with COPD or asthma (Figure 1). However, there is no evidence that this higher exposure to fluticasone furoate results in clinically relevant effects on urinary cortisol excretion or on efficacy in these racial groups.

Vilanterol: There was no effect of race on the pharmacokinetics of vilanterol in patients with COPD. In patients with asthma, vilanterol Cmax is estimated to be higher (3-fold) and AUC(0-24) comparable for those patients from an Asian heritage compared with patients from a non-Asian heritage. However, the higher Cmax values are similar to those seen in healthy subjects.

Patients with Hepatic Impairment: Fluticasone Furoate: Following repeat dosing of fluticasone furoate/vilanterol 200/25 mcg (100/12.5 mcg in the severe impairment group) for 7 days, there was an increase of 34%, 83%, and 75% in fluticasone furoate systemic exposure (AUC) in patients with mild, moderate, and severe hepatic impairment, respectively, compared with healthy subjects (Figure 1).

In patients with moderate hepatic impairment receiving fluticasone furoate/vilanterol 200/25 mcg, mean serum cortisol (0 to 24 hours) was reduced by 34% (90% CI: 11%, 51%) compared with healthy subjects. In patients with severe hepatic impairment receiving fluticasone furoate/vilanterol 100/12.5 mcg, mean serum cortisol (0 to 24 hours) was increased by 14% (90% CI: -16%, 55%) compared with healthy subjects. Patients with moderate to severe hepatic disease should be closely monitored.

Vilanterol: Hepatic impairment had no effect on vilanterol systemic exposure [Cmax and AUC(0-24) on Day 7] following repeat-dose administration of fluticasone furoate/vilanterol 200/25 mcg (100/12.5 mcg in the severe impairment group) for 7 days (Figure 1).

There were no additional clinically relevant effects of the fluticasone furoate/vilanterol combinations on heart rate or serum potassium in patients with mild or moderate hepatic impairment (vilanterol 25 mcg combination) or with severe hepatic impairment (vilanterol 12.5 mcg combination) compared with healthy subjects.

Patients with Renal Impairment: Fluticasone furoate systemic exposure was not increased and vilanterol systemic exposure [AUC(0-24)] was 56% higher in patients with severe renal impairment compared with healthy subjects (Figure 1). There was no evidence of greater corticosteroid or beta-agonist class-related systemic effects (assessed by serum cortisol, heart rate, and serum potassium) in patients with severe renal impairment compared with healthy subjects.

Drug Interaction Studies

There were no clinically relevant differences in the pharmacokinetics or pharmacodynamics of either fluticasone furoate or vilanterol when administered in combination compared with administration alone. The potential for fluticasone furoate and vilanterol to inhibit or induce metabolic enzymes and transporter systems is negligible at low inhalation doses.

Inhibitors of Cytochrome P450 3A4: The exposure (AUC) of fluticasone furoate and vilanterol were 36% and 65% higher, respectively, when coadministered with ketoconazole 400 mg compared with placebo (Figure 2). The increase in fluticasone furoate exposure was associated with a 27% reduction in weighted mean serum cortisol (0 to 24 hours). The increase in vilanterol exposure was not associated with an increase in beta-agonist–related systemic effects on heart rate or blood potassium.

Figure 2. Impact of Coadministered Drugsa on the Pharmacokinetics (PK) of Fluticasone Furoate (FF) and Vilanterol (VI) Following Administration as Fluticasone Furoate/Vilanterol Combination or Vilanterol Coadministered with a Long-Acting Muscarinic Antagonist

aCompared with placebo group.

Inhibitors of P-glycoprotein: Fluticasone furoate and vilanterol are both substrates of P-glycoprotein (P-gp). Coadministration of repeat-dose (240 mg once daily) verapamil (a moderate CYP3A4 inhibitor and a P-gp inhibitor) did not affect the vilanterol Cmax or AUC in healthy subjects (Figure 2). Drug interaction trials with a specific P-gp inhibitor and fluticasone furoate have not been conducted.

13 NONCLINICAL TOXICOLOGY

13.1 Carcinogenesis, Mutagenesis, Impairment of Fertility

BREO ELLIPTA

No studies of carcinogenicity, mutagenicity, or impairment of fertility were conducted with BREO ELLIPTA; however, studies are available for the individual components, fluticasone furoate and vilanterol, as described below.

Fluticasone Furoate

Fluticasone furoate produced no treatment-related increases in the incidence of tumors in 2-year inhalation studies in rats and mice at inhaled doses up to 9 and 19 mcg/kg/day, respectively (both approximately 0.5 times the MRHDID of 200 mcg on a mcg/m^2 basis).

Fluticasone furoate did not induce gene mutation in bacteria or chromosomal damage in a mammalian cell mutation test in mouse lymphoma L5178Y cells in vitro. There was also no evidence of genotoxicity in the in vivo micronucleus test in rats.

No evidence of impairment of fertility was observed in male and female rats at inhaled fluticasone furoate doses up to 29 and 91 mcg/kg/day, respectively (approximately 3 and 8 times, respectively, the MRHDID of 200 mcg for adults on an AUC basis).

Vilanterol

In a 2-year carcinogenicity study in mice, vilanterol caused a statistically significant increase in ovarian tubulostromal adenomas in females at an inhaled dose of 29,500 mcg/kg/day (approximately 8,750 times the MRHDID on an AUC basis). No increase in tumors was seen at an inhaled dose of 615 mcg/kg/day (approximately 530 times the MRHDID on an AUC basis).

In a 2-year carcinogenicity study in rats, vilanterol caused statistically significant increases in mesovarian leiomyomas in females and shortening of the latency of pituitary tumors at inhaled doses greater than or equal to 84.4 mcg/kg/day (greater than or equal to approximately 45 times the MRHDID on an AUC basis). No tumors were seen at an inhalation dose of 10.5 mcg/kg/day (approximately 2 times the MRHDID on an AUC basis).

These tumor findings in rodents are similar to those reported previously for other beta-adrenergic agonist drugs. The relevance of these findings to human use is unknown.

Vilanterol tested negative in the following genotoxicity assays: the in vitro Ames assay, in vivo rat bone marrow micronucleus assay, in vivo rat unscheduled DNA synthesis (UDS) assay, and in vitro Syrian hamster embryo (SHE) cell assay. Vilanterol tested equivocal in the in vitro mouse lymphoma assay.

No evidence of impairment of fertility was observed in male and female rats at inhaled vilanterol doses up to 31,500 and 37,100 mcg/kg/day, respectively (both approximately 5,490 times the MRHDID based on AUC).

14 CLINICAL STUDIES

14.1 Chronic Obstructive Pulmonary Disease

Four trials evaluated the efficacy of BREO ELLIPTA on lung function (Trial 1, NCT01053988 and Trial 2, NCT01054885) and exacerbations (Trial 3, NCT01009463 and Trial 4, NCT01017952).

Lung Function: Trials 1 and 2 were 24-week, randomized, double-blind, placebo-controlled trials designed to evaluate the efficacy of BREO ELLIPTA on lung function in patients with COPD. In Trial 1, patients were randomized to BREO ELLIPTA 100/25 mcg, BREO ELLIPTA 200/25 mcg, fluticasone furoate 100 mcg, fluticasone furoate 200 mcg, vilanterol 25 mcg, and placebo. In Trial 2, patients were randomized to BREO ELLIPTA 100/25 mcg, fluticasone furoate/vilanterol 50/25 mcg, fluticasone furoate 100 mcg, vilanterol 25 mcg, and placebo. All treatments were administered as 1 inhalation once daily.

Of the 2,254 patients, 70% were male and 84% were White. They had a mean age of 62 years and an average smoking history of 44 pack years, with 54% identified as current smokers. At screening, the mean postbronchodilator percent predicted FEV1 was 48% (range: 14% to 87%), mean postbronchodilator FEV1/FVC ratio was 47% (range: 17% to 88%), and the mean percent reversibility was 14% (range: -41% to 152%).

The co-primary efficacy variables in both trials were weighted mean FEV1 (0 to 4 hours) postdose on Day 168 and change from baseline in trough FEV1 on Day 169 (the mean of the FEV1 values obtained 23 and 24 hours after the final dose on Day 168). The weighted mean comparison of the fluticasone furoate/vilanterol combination with fluticasone furoate was assessed to evaluate the contribution of vilanterol to BREO ELLIPTA. The trough FEV1 comparison of the fluticasone furoate/vilanterol combination with vilanterol was assessed to evaluate the contribution of fluticasone furoate to BREO ELLIPTA.

BREO ELLIPTA 100/25 mcg demonstrated a larger increase in the weighted mean FEV1 (0 to 4 hours) relative to placebo and fluticasone furoate 100 mcg at Day 168 (Table 6).

Table 6. Least Squares Mean Change from Baseline in Weighted Mean FEV1 (0-4 h) and Trough FEV1 at 6 Months
Treatment | N | Weighted Mean FEV1 (0-4 h)a (mL) |  |  | Trough FEV1b (mL)
Treatment | N | Difference from |  |  | Difference from
Treatment | N | Placebo; (95% CI) | Fluticasone Furoate; 100 mcg; (95% CI) | Fluticasone Furoate; 200 mcg; (95% CI) | Placebo (95% CI) | Vilanterol; 25 mcg; (95% CI)
Trial 1
BREO ELLIPTA 100/25 mcg | 204 | 214; (161, 266) | 168; (116, 220) | –– | 144; (91, 197) | 45; (-8, 97)
BREO ELLIPTA 200/25 mcg | 205 | 209; (157, 261) | –– | 168; (117, 219) | 131; (80, 183) | 32; (-19, 83)
Trial 2
BREO ELLIPTA 100/25 mcg | 206 | 173; (123, 224) | 120; (70, 170) | –– | 115; (60, 169) | 48; (-6, 102)
FEV1 = Forced Expiratory Volume in 1 second.
a At Day 168.
b At Day 169.

Serial spirometric evaluations were performed predose and up to 4 hours after dosing. Results from Trial 1 at Day 1 and Day 168 are shown in Figure 3. Similar results were seen in Trial 2 (not shown).

Figure 3. Raw Mean Change from Baseline in Postdose Serial FEV1 (0-4 h) (mL) on Days 1 and 168

Day 1

Day 168

The second co-primary variable was change from baseline in trough FEV1 following the final treatment day. At Day 169, both Trials 1 and 2 demonstrated significant increases in trough FEV1 for all strengths of the fluticasone furoate/vilanterol combination compared with placebo (Table 7). The comparison of BREO ELLIPTA 100/25 mcg with vilanterol did not achieve statistical significance (Table 7).

Trials 1 and 2 evaluated FEV1 as a secondary endpoint. Peak FEV1 was defined as the maximum postdose FEV1 recorded within 4 hours after the first dose of trial medicine on Day 1 (measurements recorded at 5, 15, and 30 minutes and 1, 2, and 4 hours). In both trials, differences in mean change from baseline in peak FEV1 were observed for the groups receiving BREO ELLIPTA 100/25 mcg compared with placebo (152 and 139 mL, respectively). The median time to onset, defined as a 100-mL increase from baseline in FEV1, was 16 minutes in patients receiving BREO ELLIPTA 100/25 mcg.

Exacerbations: Trials 3 and 4 were randomized, double-blind, 52-week trials designed to evaluate the effect of BREO ELLIPTA on the rate of moderate and severe COPD exacerbations. All patients were treated with fluticasone propionate/salmeterol 250/50 mcg twice daily during a 4-week run-in period prior to being randomly assigned to 1 of the following treatment groups: BREO ELLIPTA 100/25 mcg, BREO ELLIPTA 200/25 mcg, fluticasone furoate/vilanterol 50/25 mcg, or vilanterol 25 mcg.

The primary efficacy variable in both trials was the annual rate of moderate/severe exacerbations. The comparison of the fluticasone furoate/vilanterol combination with vilanterol was assessed to evaluate the contribution of fluticasone furoate to BREO ELLIPTA. In these 2 trials, exacerbations were defined as worsening of 2 or more major symptoms (dyspnea, sputum volume, and sputum purulence) or worsening of any 1 major symptom together with any 1 of the following minor symptoms: sore throat, colds (nasal discharge and/or nasal congestion), fever without other cause, and increased cough or wheeze for at least 2 consecutive days. COPD exacerbations were considered to be of moderate severity if treatment with systemic corticosteroids and/or antibiotics was required and were considered to be severe if hospitalization was required.

Trials 3 and 4 included 3,255 patients, of which 57% were male and 85% were White. They had a mean age of 64 years and an average smoking history of 46 pack years, with 44% identified as current smokers. At screening, the mean postbronchodilator percent predicted FEV1 was 45% (range: 12% to 91%), and mean postbronchodilator FEV1/FVC ratio was 46% (range: 17% to 81%), indicating that the patient population had moderate to very severely impaired airflow obstruction. The mean percent reversibility was 15% (range: -65% to 313%).

Patients treated with BREO ELLIPTA 100/25 mcg had a lower annual rate of moderate/severe COPD exacerbations compared with vilanterol in both trials (Table 7).

Table 7. Moderate and Severe Chronic Obstructive Pulmonary Disease Exacerbations
Treatment | n | Mean Annual Rate; (exacerbations/year) | Ratio vs. Vilanterol | 95% CI
Trial 3
BREO ELLIPTA 100/25 mcg | 403 | 0.90 | 0.79 | 0.64, 0.97
BREO ELLIPTA 200/25 mcg | 409 | 0.79 | 0.69 | 0.56, 0.85
Fluticasone furoate/vilanterol 50/25 mcg | 412 | 0.92 | 0.81 | 0.66, 0.99
Vilanterol 25 mcg | 409 | 1.14 | –– | ––
Trial 4
BREO ELLIPTA 100/25 mcg | 403 | 0.70 | 0.66 | 0.54, 0.81
BREO ELLIPTA 200/25 mcg | 402 | 0.90 | 0.85 | 0.70, 1.04
Fluticasone furoate/vilanterol 50°/25 mcg | 408 | 0.92 | 0.87 | 0.72, 1.06
Vilanterol 25 mcg | 409 | 1.05 | –– | ––

Comparator Trials

Three 12-week, randomized, double-blind, double-dummy trials were conducted with BREO ELLIPTA 100/25 mcg once daily versus fluticasone propionate/salmeterol 250/50 mcg twice daily to evaluate the efficacy of serial lung function of BREO ELLIPTA in patients with COPD. The primary endpoint of each trial was change from baseline in weighted mean FEV1 (0 to 24 hours) on Day 84. Of the 519 patients in Trial 5 (NCT01323634), 64% were male and 97% were White; mean age was 61 years; average smoking history was 40 pack years, with 55% identified as current smokers. At screening in the treatment group using BREO ELLIPTA 100/25 mcg, the mean postbronchodilator percent predicted FEV1 was 48% (range: 19% to 70%), the mean (SD) FEV1/FVC ratio was 0.51 (0.11), and the mean percent reversibility was 11% (range: -12% to 83%). At screening in the treatment group using fluticasone propionate/salmeterol 250/50 mcg, the mean postbronchodilator percent predicted FEV1 was 47% (range: 14% to 71%), the mean (SD) FEV1/FVC ratio was 0.49 (0.10), and the mean percent reversibility was 11% (range: -13% to 50%).

Of the 511 patients in Trial 6 (NCT01323621), 68% were male and 94% were White; mean age was 62 years; average smoking history was 35 pack years, with 52% identified as current smokers. At screening in the treatment group using BREO ELLIPTA 100/25 mcg, the mean postbronchodilator percent predicted FEV1 was 48% (range: 18% to 70%), the mean (SD) FEV1/FVC ratio was 0.51 (0.10), and the mean percent reversibility was 12% (range: -56% to 77%). At screening in the treatment group using fluticasone propionate/salmeterol 250/50 mcg, the mean postbronchodilator percent predicted FEV1 was 49% (range: 15% to 70%), the mean (SD) FEV1/FVC ratio was 0.50 (0.10), and the mean percent reversibility was 12% (range: -66% to 72%).

Of the 828 patients in Trial 7 (NCT01706328), 72% were male and 98% were White; mean age was 61 years; average smoking history was 38 pack years, with 60% identified as current smokers. At screening in the treatment group using BREO ELLIPTA 100/25 mcg, the mean postbronchodilator percent predicted FEV1 was 48% (range: 18% to 70%), the mean (SD) FEV1/FVC ratio was 0.52 (0.10), and the mean percent reversibility was 12% (range: -26% to 84%). At screening in the treatment group using fluticasone propionate/salmeterol 250/50 mcg, the mean postbronchodilator percent predicted FEV1 was 48% (range: 16% to 70%), the mean (SD) FEV1/FVC ratio was 0.51 (0.10), and the mean percent reversibility was 12% (range: -15% to 67%).

In Trial 5, the mean (SE) change from baseline in weighted mean FEV1 (0 to 24 hours) with BREO ELLIPTA 100/25 mcg was 174 (15) mL compared with 94 (16) mL with fluticasone propionate/salmeterol 250/50 mcg (treatment difference 80 mL; 95% CI: 37, 124; P<0.001). In Trials 6 and 7, the mean (SE) change from baseline in weighted mean FEV1 (0 to 24 hours) with BREO ELLIPTA 100/25 mcg was 142 (18) mL and 168 (12) mL, respectively, compared with 114 (18) mL and 142 (12) mL, respectively, for fluticasone propionate/salmeterol 250/50 mcg (Trial 6 treatment difference 29 mL; 95% CI: -22, 80; P = 0.267; Trial 7 treatment difference 25 mL; 95% CI: -8, 59; P = 0.137).

Mortality Trial

A randomized, double-blind, multicenter, multinational trial (NCT01313676) prospectively evaluated the efficacy of BREO ELLIPTA 100/25 mcg compared with placebo on survival. The trial was event-driven, and patients were followed until a sufficient number of deaths occurred. In this trial, 16,568 patients aged 40 to 80 years received BREO ELLIPTA 100/25 mcg (n = 4,140), fluticasone furoate 100 mcg (n = 4,157), vilanterol 25 mcg (n = 4,140), or placebo (n = 4,131). Patients were treated for up to 4 years, with a median treatment duration of 1.5 years. Median duration of follow-up for the endpoint of survival was 1.8 years for all treatment groups. All patients had COPD with moderate airflow limitation (≥50% and ≤70% predicted FEV1) and either had a history of, or were at risk of, cardiovascular disease. The primary endpoint was all-cause mortality. Secondary efficacy endpoints included the rate of decline in FEV1, annual rate of moderate/severe COPD exacerbations, and health-related quality of life as measured by the St. George’s Respiratory Questionnaire for COPD patients (SGRQ-C).

Survival: Survival with BREO ELLIPTA 100/25 mcg was not significantly improved compared with placebo (hazard ratio 0.88; 95% CI: 0.74, 1.04). Mortality per 100 patient-years was 3.1 for BREO ELLIPTA 100/25 mcg, 3.5 for placebo, 3.2 for fluticasone furoate, and 3.4 for vilanterol.

Lung Function: A reduction of 8 mL/year was estimated on-treatment for BREO ELLIPTA 100/25 mcg compared with placebo in the rate of lung function decline as measured by FEV1 (95% CI: 1, 15).

Exacerbations: Treatment with BREO ELLIPTA 100/25 mcg reduced the on-treatment annual rate of moderate/severe exacerbations by 29% compared with placebo (95% CI: 22, 35). Treatment with BREO ELLIPTA 100/25 mcg reduced the annual rate of moderate/severe exacerbations by 19% compared with fluticasone furoate (95% CI: 12, 26) and by 21% compared with vilanterol (95% CI: 14, 28). The on-treatment annual rate of moderate/severe exacerbations was 0.25 for BREO ELLIPTA 100/25 mcg, 0.35 for placebo, 0.31 for fluticasone furoate, and 0.31 for vilanterol.

Treatment with BREO ELLIPTA 100/25 mcg reduced the on-treatment annual rate of severe exacerbations (i.e., requiring hospitalization) by 27% compared with placebo (95% CI: 13, 39). Treatment with BREO ELLIPTA 100/25 mcg reduced the on-treatment annual rate of exacerbations requiring hospitalization by 11% compared with fluticasone furoate (95% CI: -6, 25) and by 9% compared with vilanterol (95% CI: -8, 24).

Health-Related Quality of Life: The St. George’s Respiratory Questionnaire (SGRQ) is a disease-specific patient-reported instrument that measures symptoms, activities, and impact on daily life. The SGRQ-C, a shorter version derived from the original SGRQ, was used in this trial. Results were transformed to the SGRQ for reporting purposes. In a subset of 4,443 patients, the on-treatment SGRQ responder rates at 1 year (defined as a change in score of 4 or more as threshold) were 49% for BREO ELLIPTA 100/25 mcg, 47% for placebo, 48% for fluticasone furoate, and 48% for vilanterol (odds ratio 1.18; 95% CI: 0.97, 1.44 for BREO ELLIPTA 100/25 mcg compared with placebo).

14.2 Asthma

Adult Patients

The efficacy of BREO ELLIPTA for the maintenance treatment of asthma was based on data from 4 randomized, double-blind, parallel-group clinical trials (Trial 8 [NCT01165138], Trial 9 [NCT01686633], Trial 10 [NCT01134042] and Trial 12 [NCT01086384]). While these 4 trials enrolled pediatric patients 12 to 17 years of age, these trials only support efficacy in adults [see Use in Specific Populations (8.4)]. In addition, patients in these trials were treated with BREO ELLIPTA 200/25 mcg once daily by oral inhalation, which is not the approved recommended dosage for pediatric patients 12 years of age and older [see Dosage and Administration (2.2)]. Trials 8, 9, and 10 were designed to evaluate the safety and efficacy of BREO ELLIPTA given once daily in patients who were not controlled on their current treatments of ICS or combination therapy consisting of an ICS plus a LABA. Trial 12 (24- to 76-week exacerbation trial) was designed to demonstrate that treatment with BREO ELLIPTA 100/25 mcg significantly decreased the risk of asthma exacerbations as measured by time to first asthma exacerbation when compared with fluticasone furoate 100 mcg. This trial enrolled patients who had 1 or more asthma exacerbations in the year prior to trial entry. The demographics of these 4 trials and the comparator trial (Trial 13, NCT01147848) are provided in Table 8.

Table 8. Demography of Asthma Trials 8, 9, 10, 12, and 13
Parameter | Trial 8; n = 609 | Trial 9; n = 1,039 | Trial 10; n = 586 | Trial 12; n = 2,019 | Trial 13; n = 806
Mean age (years) (range) for all patients | 40 (12, 84) | 46 (12, 82) | 46 (12, 76) | 42 (12, 82) | 43 (12, 80)
Mean age (years) (range) for adult patients | 44 (18, 84) | 48 (18, 82) | 47 (18, 76) | 46 (18, 82) | 46 (18, 80)
Female (%) | 58 | 60 | 59 | 67 | 61
White (%) | 84 | 88 | 84 | 73 | 59
Duration of asthma (years) | 12 | 18 | 16 | 16 | 21
Never smokeda (%) | N/A | 84 | N/A | 86 | 81
Predose FEV1 (L) at baseline | 2.32 | 1.97 | 2.15 | 2.20 | 2.03
Mean percent predicted FEV1 at baseline (%) | 70 | 62 | 67 | 72 | 68
% Reversibility | 29 | 30 | 29 | 24 | 28
Absolute reversibility (mL) | 614 | 563 | 571 | 500 | 512
N/A = Data not collected.
a Trials did not include current smokers; past smokers had fewer than 10 packs per year history.

Trials 8, 9, and 10 were 12- or 24-week trials that evaluated the efficacy of BREO ELLIPTA on lung function in patients with asthma. In Trial 8, patients were randomized to BREO ELLIPTA 100/25 mcg, fluticasone furoate 100 mcg, or placebo. In Trial 9, patients were randomized to BREO ELLIPTA 100/25 mcg, BREO ELLIPTA 200/25 mcg, or fluticasone furoate 100 mcg. In Trial 10, patients were randomized to BREO ELLIPTA 200/25 mcg, fluticasone furoate 200 mcg, or fluticasone propionate 500 mcg. All inhalations were administered once daily, with the exception of fluticasone propionate, which was administered twice daily. Patients receiving an ICS or an ICS plus a LABA (doses of ICS varied by trial and asthma severity) entered a 4-week run-in period during which LABA treatment was stopped. Patients reporting symptoms and/or rescue beta2-agonist medication use during the run-in period were continued in the trial.

In Trials 8 and 10, change from baseline in weighted mean FEV1 (0 to 24 hours) and change from baseline in trough FEV1 at approximately 24 hours after the last dose at study endpoint (12 and 24 weeks, respectively) were co-primary efficacy endpoints. In Trial 9, change from baseline in weighted mean FEV1 (0 to 24 hours) at Week 12 was the primary efficacy endpoint; change from baseline in trough FEV1 at approximately 24 hours after the last dose at Week 12 was a secondary endpoint. Table 9 provides the change from baseline in weighted mean FEV1 in mL (0 to 24 hours) and trough FEV1 in mL at study endpoint. Weighted mean FEV1 (0 to 24 hours) was derived from serial measurements taken within 30 minutes prior to dosing and post-dose assessments at 5, 15, and 30 minutes and 1, 2, 3, 4, 5, 12, 16, 20, 23, and 24 hours after the final dose. Other secondary endpoints included change from baseline in percentage of rescue-free 24-hour periods and percentage of symptom-free 24-hour periods over the treatment period.

Table 9. Change from Baseline in Weighted Mean FEV1 (0-24 h) (mL) and Trough FEV1 (mL) at Study Endpoint (Trials 8, 9, and 10)a
Study (Duration); Background Treatment | n | Weighted Mean FEV1 (0-24 h) (mL)
Study (Duration); Background Treatment | n | Difference from
Study (Duration); Background Treatment | Treatment | Placebo; (95% CI) | Fluticasone Furoate 100 mcg; (95% CI) | Fluticasone Furoate 200 mcg; (95% CI)
Trial 8 (12 Weeks)
Low- to mid-dose ICS or low-dose ICS + LABA
BREO ELLIPTA 100/25 mcg | 108 | 302; (178, 426) | 116; (-5, 236) | ––
Trial 9 (12 Weeks)
Mid- to high-dose ICS or mid-dose ICS + LABA
BREO ELLIPTA 100/25 mcg | 312 | –– | 108; (45, 171) | ––
Trial 10 (24 Weeks)
High-dose ICS or mid-dose ICS + LABA
BREO ELLIPTA 200/25 mcg | 89 | –– | –– | 136; (1, 270)
Study (Duration); Background Treatment | n | Trough FEV1 (mL)
Study (Duration); Background Treatment | n | Difference from
Study (Duration); Background Treatment | Treatment | Placebo; (95% CI) | Fluticasone Furoate 100 mcg; (95% CI) | Fluticasone Furoate 200 mcg; (95% CI)
Trial 8 (12 Weeks)
Low- to mid-dose ICS or low-dose ICS + LABA
BREO ELLIPTA 100/25 mcg | 200 | 172; (87, 258) | 36; (-48, 120) | ––
Trial 9 (12 Weeks)
Mid- to high-dose ICS or mid-dose ICS + LABA
BREO ELLIPTA 100/25 mcg | 334 | –– | 77; (16, 138) | ––
Trial 10 (24 Weeks)
High-dose ICS or mid-dose ICS + LABA
BREO ELLIPTA 200/25 mcg | 187 | –– | –– | 193; (108, 277)
FEV1 = Forced Expiratory Volume in 1 second, ICS = Inhaled Corticosteroid, LABA = Long-acting Beta2-adrenergic Agonist.
a Although these trials included pediatric patients 12 to 17 years of age, they only support the efficacy in adult patients.

In Trial 8, weighted mean FEV1 (0 to 24 hours) was assessed in a subset of patients (n = 309). At Week 12, change from baseline in weighted mean FEV1 (0 to 24 hours) was significantly greater for BREO ELLIPTA 100/25 mcg compared with placebo (302 mL; 95% CI: 178, 426; P<0.001) (Table 9); change from baseline in weighted mean FEV1 (0 to 24 hours) for BREO ELLIPTA 100/25 mcg was numerically greater than fluticasone furoate 100 mcg, but not statistically significant (116 mL; 95% CI: -5, 236). At Week 12, change from baseline in trough FEV1 was significantly greater for BREO ELLIPTA 100/25 mcg compared with placebo (172 mL; 95% CI: 87, 258; P<0.001) (Table 9); change from baseline in trough FEV1 for BREO ELLIPTA 100/25 mcg was numerically greater than fluticasone furoate 100 mcg, but not statistically significant (36 mL; 95% CI: -48, 120).

In Trial 9, the change from baseline in weighted mean FEV1 (0 to 24 hours) was significantly greater for BREO ELLIPTA 100/25 mcg compared with fluticasone furoate 100 mcg (108 mL; 95% CI: 45, 171; P<0.001) at Week 12 (Table 9). In a descriptive analysis, the change from baseline in weighted mean FEV1 (0 to 24 hours) for BREO ELLIPTA 200/25 mcg was numerically greater than BREO ELLIPTA 100/25 mcg (24 mL; 95% CI: -37, 86) at Week 12. The change from baseline in trough FEV1 was significantly greater for BREO ELLIPTA 100/25 mcg compared with fluticasone furoate 100 mcg (77 mL, 95% CI: 16, 138; P = 0.014) at Week 12 (Table 9). In a descriptive analysis, the change from baseline in trough FEV1 for BREO ELLIPTA 200/25 mcg was numerically greater than BREO ELLIPTA 100/25 mcg (16 mL; 95% CI: -46, 77) at Week 12.

In Trial 10, the change from baseline in weighted mean FEV1 (0 to 24 hours) was significantly greater for BREO ELLIPTA 200/25 mcg compared with fluticasone furoate 200 mcg (136 mL; 95% CI: 1, 270; P = 0.048) at Week 24 (Table 9). The change from baseline in trough FEV1 was significantly greater for BREO ELLIPTA 200/25 mcg compared with fluticasone furoate 200 mcg (193 mL, 95% CI: 108, 277; P<0.001) at Week 24.

Lung function improvements were demonstrated through weighted mean FEV1 (0 to 24 hours) over the 24-hour period following the final dose of BREO ELLIPTA in Trials 9 and 10. Serial FEV1 measurements were taken within 30 minutes prior to dosing and postdose assessments at 5, 15, and 30 minutes and 1, 2, 3, 4, 5, 12, 16, 20, 23, and 24 hours in Trials 1, 2, and 3. A representative figure is shown from Trial 9 in Figure 4.

Figure 4. Least Squares (LS) Mean Change from Baseline in Individual Serial FEV1 (mL) Assessments over 24 Hours after 12 Weeks of Treatment (Trial 9)a

a Although these trials included pediatric patients 12 to 17 years of age, the data only support the efficacy in adult patients.

Patients receiving BREO ELLIPTA 100/25 mcg (Trial 9) or BREO ELLIPTA 200/25 mcg (Trial 10) had significantly greater improvements from baseline in percentage of 24-hour periods without need of beta2-agonist rescue medication use and percentage of 24-hour periods without asthma symptoms compared with patients receiving fluticasone furoate 100 mcg or fluticasone furoate 200 mcg, respectively. In a descriptive analysis (Trial 9), patients receiving BREO ELLIPTA 200/25 mcg had numerical improvements from baseline in percentage of 24-hour periods without need of beta2-agonist rescue medication use and percentage of 24-hour periods without asthma symptoms compared with patients receiving BREO ELLIPTA 100/25 mcg.

Trial 12 was a 24- to 76-week event-driven exacerbation trial that evaluated whether BREO ELLIPTA 100/25 mcg significantly decreased the risk of asthma exacerbations as measured by time to first asthma exacerbation when compared with fluticasone furoate 100 mcg in patients with asthma. Patients receiving low- to high-dose ICS (fluticasone propionate 100 mcg to 500 mcg twice daily or equivalent) or low- to mid-dose ICS plus a LABA (fluticasone propionate/salmeterol 100/50 mcg to 250/50 mcg twice daily or equivalent) and a history of 1 or more asthma exacerbations that required treatment with oral/systemic corticosteroid or emergency department visit or in-patient hospitalization for the treatment of asthma in the year prior to trial entry, entered a 2-week run-in period during which LABA treatment was stopped. Patients reporting symptoms and/or rescue beta2-agonist medication use during the run-in period were continued in the trial.

The primary endpoint was time to first asthma exacerbation. Asthma exacerbation was defined as deterioration of asthma requiring the use of systemic corticosteroid for at least 3 days or an in‑patient hospitalization or emergency department visit due to asthma that required systemic corticosteroid. Rate of asthma exacerbation was a secondary endpoint. The hazard ratio from the Cox Model for the analysis of time to first asthma exacerbation for BREO ELLIPTA 100/25 mcg compared with fluticasone furoate 100 mcg was 0.795 (95% CI: 0.642, 0.985). This represents a 20% reduction in the risk of experiencing an asthma exacerbation for patients treated with BREO ELLIPTA 100/25 mcg compared with fluticasone furoate 100 mcg (P = 0.036). Mean yearly rates of asthma exacerbations of 0.14 and 0.19 in patients treated with BREO ELLIPTA 100/25 mcg compared with fluticasone furoate 100 mcg, respectively, were observed (25% reduction in rate; 95% CI: 5%, 40%).

Comparator Trial

Trial 13 was a 24-week trial that compared the efficacy of BREO ELLIPTA 100/25 mcg once daily with fluticasone propionate/salmeterol 250/50 mcg twice daily (N = 806). Patients receiving mid-dose ICS (fluticasone propionate 250 mcg twice daily or equivalent) entered a 4-week run-in period during which all patients received fluticasone propionate 250 mcg twice daily. The primary endpoint was change from baseline in weighted mean FEV1 (0 to 24 hours) at Week 24.

The mean change (SE) from baseline in weighted mean FEV1 (0 to 24 hours) for BREO ELLIPTA 100/25 mcg was 341 (18.4) mL compared with 377 (18.5) mL for fluticasone propionate/salmeterol 250/50 mcg (treatment difference -37 mL; 95% CI: -88, 15; P = 0.162).

Pediatric Patients Aged 5 to 17 Years

The efficacy of BREO ELLIPTA for the maintenance treatment of asthma in pediatric patients aged 5 to 17 years of age was based on Trial 14 (NCT03248128), a 24-week, randomized, double-blind, stratified, parallel-group clinical trial. This trial evaluated the efficacy of BREO ELLIPTA compared with fluticasone furoate in 902 pediatric patients with asthma aged 5 to 17 years who were uncontrolled on their current ICS treatment. All inhalations were administered once daily in the morning. At trial entry patients had at least a 6-month history of asthma and had been receiving stable asthma therapy for at least 4 weeks prior to screening. Patients had to have a pre-bronchodilator FEV1 >50% to ≤100% of predicted normal and demonstrate a ≥12% reversibility of FEV1 within 15 to 40 minutes following 2 to 4 inhalations of albuterol inhalation aerosol (or 1 nebulized treatment with albuterol solution). Exclusion criteria included a history of life-threatening asthma or any asthma exacerbation requiring the use of oral corticosteroids, systemic or depot corticosteroids, emergency department visit, or hospitalization within 6 weeks, 3 months, or 6 months of screening, respectively.

Patients entered a 4-week open-label run-in period during which all patients received fluticasone propionate 100 mcg twice daily. Patients reporting symptoms and/or rescue beta2-agonist medication use during the last week of the run-in period were continued in the trial and were stratified by age. Pediatric patients aged 12 to 17 years (n = 229) were randomized 1:1 to BREO ELLIPTA 100/25 mcg once daily (n = 117) or fluticasone furoate 100 mcg once daily (n = 112). Pediatric patients aged 5 to 11 years (n = 673) were randomized 1:1 to BREO ELLIPTA 50/25 mcg once daily (n = 337) or fluticasone furoate 50 mcg once daily (n = 336). The primary endpoint was weighted mean FEV1 (0 to 4 hours) at Week 12. Of the 902 patients, the mean age was 10.0 years, 61% were male, and 73% were White, 8% African American, 6% American Indian or Alaska Native, 6% Asian, and 7% Other. Lung function improvements based on the primary endpoint of weighted mean FEV1 (0 to 4 hours) are presented in Table 10.

Table 10. Weighted Mean FEV1 (0-4 h) (mL) at Week 12 in Patients Aged 5 to 17 Years (Intent to Treat Population)
Primary Endpoint | Fluticasone Furoatea; (N = 448) | BREO ELLIPTAb; (N = 454)
Weighted Mean FEV1 (0-4 h) (mL) | n = 397 | n = 394
LS mean | 1999 | 2081
LS mean change (SE) | 323 (16.4) | 406 (16.5)
Difference vs fluticasone furoate |  | 83
(95% CI) |  | (37, 129)
FEV1 = Forced Expiratory Volume in 1 second, LS = Least Squares, SE = Standard Error.

a The dose of fluticasone furoate was 100 mcg once daily for pediatric patients aged 12 to 17 years and 50 mcg once daily for pediatric patients aged 5 to 11 years.
b The dose of BREO ELLIPTA was 100/25 mcg once daily for pediatric patients aged 12 to 17 years and 50/25 mcg once daily for pediatric patients aged 5 to 11 years.

Difference in LS mean change from baseline at Week 12 for BREO ELLIPTA 100/25 mcg compared with fluticasone furoate 100 mcg was 106 mL (95% CI: -8, 220) in pediatric patients 12 to 17 years of age, and difference in LS mean change from baseline at Week 12 for BREO ELLIPTA 50/25 mcg compared with fluticasone furoate 50 mcg was 73 mL (95% CI: 28, 118) in pediatric patients 5 to 11 years of age.

16 HOW SUPPLIED/STORAGE AND HANDLING

BREO ELLIPTA is supplied as a disposable light grey and pale blue plastic inhaler containing 2 foil strips, each with 30 blisters (or 14 blisters for the institutional pack). One strip contains fluticasone furoate (50, 100 or 200 mcg per blister), and the other strip contains vilanterol (25 mcg per blister). A blister from each strip is used to create 1 dose. The inhaler is packaged within a moisture-protective foil tray with a desiccant and a peelable lid in the following packs:

NDC 0173-0916-10 BREO ELLIPTA 50/25 mcg 30 inhalations (60 blisters)
NDC 0173-0859-10 BREO ELLIPTA 100/25 mcg 30 inhalations (60 blisters)
NDC 0173-0859-14 BREO ELLIPTA 100/25 mcg 14 inhalations (28 blisters), institutional pack
NDC 0173-0882-10 BREO ELLIPTA 200/25 mcg 30 inhalations (60 blisters)
NDC 0173-0882-14 BREO ELLIPTA 200/25 mcg 14 inhalations (28 blisters), institutional pack

Store at room temperature between 68°F and 77°F (20°C and 25°C); excursions permitted from 59°F to 86°F (15°C to 30°C) [See USP Controlled Room Temperature]. Store in a dry place away from direct heat or sunlight. Keep out of reach of children.

BREO ELLIPTA should be stored inside the unopened moisture-protective foil tray and only removed from the tray immediately before initial use. Discard BREO ELLIPTA 6 weeks after opening the foil tray or when the counter reads “0” (after all blisters have been used), whichever comes first. The inhaler is not reusable. Do not attempt to take the inhaler apart.

17 PATIENT COUNSELING INFORMATION

Advise the patient to read the FDA-approved patient labeling (Patient Information and Instructions for Use).

Serious Asthma-Related Events

Inform patients with asthma that LABA when used alone increases the risk of asthma-related hospitalization or asthma-related death. Available data show that when ICS and LABA are used together, such as with BREO ELLIPTA, there is not a significant increase in the risk of these events. [See Warnings and Precautions (5.1).]

Not for Acute Symptoms

Inform patients that BREO ELLIPTA is not meant to relieve acute symptoms of COPD or asthma and extra doses should not be used for that purpose. Advise patients to treat acute symptoms with an inhaled, short-acting beta2-agonist such as albuterol. Provide patients with such medication and instruct them in how it should be used.

Instruct patients to seek medical attention immediately if they experience any of the following:

- Decreasing effectiveness of inhaled, short-acting beta2-agonists
- Need for more inhalations than usual of inhaled, short-acting beta2-agonists
- Significant decrease in lung function as outlined by the physician

Tell patients they should not stop therapy with BREO ELLIPTA without physician/provider guidance since symptoms may recur after discontinuation. [See Warnings and Precautions (5.2).]

Do Not Use Additional Long-Acting Beta2-Agonists

Instruct patients not to use other LABA for COPD and asthma. [See Warnings and Precautions (5.3).]

Oropharyngeal Candidiasis

Inform patients that localized infections with Candida albicans occurred in the mouth and pharynx in some patients. If oropharyngeal candidiasis develops, treat it with appropriate local or systemic (i.e., oral) antifungal therapy while still continuing therapy with BREO ELLIPTA, but at times therapy with BREO ELLIPTA may need to be temporarily interrupted under close medical supervision. Advise patients to rinse the mouth with water without swallowing after inhalation to help reduce the risk of thrush. [See Warnings and Precautions (5.4).]

Pneumonia

Patients with COPD have a higher risk of pneumonia; instruct them to contact their healthcare providers if they develop symptoms of pneumonia. [See Warnings and Precautions (5.5).]

Immunosuppression and Risk of Infections

Warn patients who are on immunosuppressant doses of corticosteroids to avoid exposure to chickenpox or measles and, if exposed, to consult their physicians without delay. Inform patients of potential worsening of existing tuberculosis; fungal, bacterial, viral, or parasitic infections; or ocular herpes simplex. [See Warnings and Precautions (5.6).]

Hypercorticism and Adrenal Suppression

Advise patients that BREO ELLIPTA may cause systemic corticosteroid effects of hypercorticism and adrenal suppression. Additionally, inform patients that deaths due to adrenal insufficiency have occurred during and after transfer from systemic corticosteroids. Patients should taper slowly from systemic corticosteroids if transferring to BREO ELLIPTA. [See Warnings and Precautions (5.8).]

Paradoxical Bronchospasm

As with other inhaled medicines, BREO ELLIPTA can cause paradoxical bronchospasm. If paradoxical bronchospasm occurs, instruct patients to discontinue BREO ELLIPTA and contact their healthcare provider right away. [See Warnings and Precautions (5.10).]

Hypersensitivity Reactions, including Anaphylaxis

Advise patients that hypersensitivity reactions (e.g., anaphylaxis, angioedema, rash, urticaria) may occur after administration of BREO ELLIPTA. Instruct patients to discontinue BREO ELLIPTA if such reactions occur. There have been reports of anaphylactic reactions in patients with severe milk protein allergy after inhalation of other powder medications containing lactose; therefore, patients with severe milk protein allergy should not use BREO ELLIPTA. [See Warnings and Precautions (5.11).]

Reduction in Bone Mineral Density

Advise patients who are at an increased risk for decreased BMD that the use of corticosteroids may pose an additional risk. [See Warnings and Precautions (5.13).]

Reduced Growth Velocity

Inform patients that orally inhaled corticosteroids, including fluticasone furoate, may cause a reduction in growth velocity when administered to pediatric patients. Physicians should closely follow the growth of children taking corticosteroids by any route. [See Warnings and Precautions (5.14).]

Glaucoma and Cataracts

Advise patients that long-term use of ICS may increase the risk of some eye problems (cataracts or glaucoma); consider regular eye examinations. [See Warnings and Precautions (5.15).]

Risks Associated with Beta-Agonist Therapy

Inform patients of adverse effects associated with beta2-agonists, such as palpitations, chest pain, rapid heart rate, tremor, or nervousness. Instruct patients to consult a healthcare practitioner immediately should any of these signs and symptoms develop. [See Warnings and Precautions (5.12).]

Trademarks are owned by or licensed to the GSK group of companies.

BREO ELLIPTA was developed in collaboration with Innoviva.

GlaxoSmithKline

Durham, NC 27701

©2024 GSK group of companies or its licensor.

BRE:13PI

PATIENT INFORMATION

BREO ELLIPTA (BRE-oh e-LIP-ta)

(fluticasone furoate and vilanterol inhalation powder)

for oral inhalation use

What is BREO ELLIPTA?

- BREO ELLIPTA combines 2 medicines in 1 inhaler, an inhaled corticosteroid (ICS) medicine (fluticasone furoate), and a long-acting beta2-adrenergic agonist (LABA) medicine (vilanterol).
  - ICS medicines such as fluticasone furoate help to decrease inflammation in the lungs. Inflammation in the lungs can lead to breathing problems.
  - LABA medicines such as vilanterol help the muscles around the airways in your lungs stay relaxed to prevent symptoms, such as wheezing, cough, chest tightness, and shortness of breath. These symptoms can happen when the muscles around the airways tighten. This makes it hard to breathe.
- BREO ELLIPTA is not used to relieve sudden breathing problems and will not replace a rescue inhaler.
- BREO ELLIPTA is a prescription medicine used long term (chronic) to treat people with:
Chronic Obstructive Pulmonary Disease (COPD):
  1. BREO ELLIPTA is a prescription medicine used to treat COPD. COPD is a chronic lung disease that includes chronic bronchitis, emphysema, or both.
  2. BREO ELLIPTA is used to improve symptoms of COPD for better breathing and to reduce the number of flare-ups (the worsening of your COPD symptoms for several days).
Asthma:
  1. BREO ELLIPTA is a prescription medicine used to prevent and control symptoms of asthma for better breathing and to prevent symptoms such as wheezing.
  2. BREO ELLIPTA contains vilanterol. LABA medicines such as vilanterol when used alone increase the risk of hospitalizations and death from asthma problems. BREO ELLIPTA contains an ICS and a LABA. When an ICS and LABA are used together, there is not a significant increased risk in hospitalizations and death from asthma problems.
It is not known if BREO ELLIPTA is safe and effective in children younger than 5 years of age.

Do not use BREO ELLIPTA:

- to treat sudden, severe symptoms of COPD or asthma.
- if you have a severe allergy to milk proteins. Ask your healthcare provider if you are not sure.
- if you are allergic to fluticasone furoate, vilanterol, or any of the ingredients in BREO ELLIPTA. See the end of this Patient Information for a complete list of ingredients in BREO ELLIPTA.

Before using BREO ELLIPTA, tell your healthcare provider about all of your medical conditions, including if you:

- have heart problems.
- have high blood pressure.
- have seizures.
- have thyroid problems.
- have diabetes or have been told you have high blood sugar.
- have liver problems.
- have weak bones (osteoporosis).
- have an immune system problem.
- have eye problems such as glaucoma, increased pressure in your eye, cataracts, or other changes in vision.
- are allergic to milk proteins.
- have any type of viral, bacterial, fungal, or parasitic infection.
- are exposed to chickenpox or measles.
- are pregnant or plan to become pregnant. It is not known if BREO ELLIPTA may harm your unborn baby.
- are breastfeeding or plan to breastfeed. It is not known if the medicines in BREO ELLIPTA pass into your breast milk and if they can harm your baby.

Tell your healthcare provider about all the medicines you take, including prescription and over-the-counter medicines, vitamins, and herbal supplements. BREO ELLIPTA and certain other medicines may interact with each other. This may cause serious side effects. Especially tell your healthcare provider if you take

- other LABA (including salmeterol, formoterol, arformoterol, olodaterol, and indacaterol)
- antifungal or anti-HIV medicines.

Know the medicines you take. Keep a list of them to show your healthcare provider and pharmacist when you get a new medicine.

How should I use BREO ELLIPTA?

Read the step-by-step instructions for using BREO ELLIPTA at the end of this Patient Information.

- Do not use BREO ELLIPTA unless your healthcare provider has taught you how to use the inhaler and you understand how to use it correctly.
- BREO ELLIPTA comes in 3 different strengths. Your healthcare provider prescribed the strength that is best for you.
- Use BREO ELLIPTA exactly as your healthcare provider tells you to use it. Do not use BREO ELLIPTA more often than prescribed.
- Children may need help to use BREO ELLIPTA.
- Use 1 inhalation of BREO ELLIPTA 1 time each day. Use BREO ELLIPTA at the same time each day.
- If you miss a dose of BREO ELLIPTA, take it as soon as you remember. Do not take more than 1 inhalation per day. Take your next dose at your usual time. Do not take 2 doses at 1 time.
- If you take too much BREO ELLIPTA, call your healthcare provider or go to the nearest hospital emergency room right away if you have any unusual symptoms, such as worsening shortness of breath, chest pain, increased heart rate, or shakiness.
- Do not use other medicines that contain a LABA for any reason. Ask your healthcare provider or pharmacist if any of your other medicines are LABA medicines.
- Do not stop using BREO ELLIPTA unless told to do so by your healthcare provider because your symptoms might get worse. Your healthcare provider will change your medicines as needed.
- BREO ELLIPTA does not relieve sudden symptoms of COPD or asthma and you should not take extra doses of BREO ELLIPTA to relieve these sudden symptoms. Always have a rescue inhaler with you to treat sudden symptoms. If you do not have a rescue inhaler, call your healthcare provider to have one prescribed for you.
- Call your healthcare provider or get medical care right away if:
  - your breathing problems get worse.
  - you need to use your rescue inhaler more often than usual.
  - your rescue inhaler does not work as well to relieve your symptoms.
  - your peak flow meter results decrease. Your healthcare provider will tell you the numbers that are right for you.

What are the possible side effects of BREO ELLIPTA?

BREO ELLIPTA can cause serious side effects, including:

- fungal infection in your mouth or throat (thrush). Rinse your mouth with water without swallowing after using BREO ELLIPTA to help reduce your chance of getting thrush.
- pneumonia. People with COPD have a higher chance of getting pneumonia. BREO ELLIPTA may increase the chance of getting pneumonia. Call your healthcare provider if you notice any of the following symptoms:

○increase in mucus (sputum) production
○change in mucus color
○fever

○chills
○increased cough
○increased breathing problems

- weakened immune system and increased chance of getting infections (immunosuppression).
- reduced adrenal function (adrenal insufficiency). Adrenal insufficiency is a condition where the adrenal glands do not make enough steroid hormones. This can happen when you stop taking oral corticosteroid medicines (such as prednisone) and start taking a medicine containing an ICS (such as BREO ELLIPTA). During this transition period, when your body is under stress from fever, trauma (such as a car accident), infection, surgery, or worse COPD or asthma symptoms, adrenal insufficiency can get worse and may cause death.
Symptoms of adrenal insufficiency include:

○feeling tired
○lack of energy
○weakness

○nausea and vomiting
○low blood pressure (hypotension)

- sudden breathing problems immediately after inhaling your medicine. If you have sudden breathing problems immediately after inhaling your medicine, stop using BREO ELLIPTA and call your healthcare provider right away.
- serious allergic reactions. Call your healthcare provider or get emergency medical care if you get any of the following symptoms of a serious allergic reaction:

○rash
○hives

○swelling of your face, mouth, and tongue

○breathing problems

- effects on heart.

○increased blood pressure
○a fast or irregular heartbeat, awareness of heartbeat

○chest pain

- effects on nervous system.

○tremor

○nervousness

- bone thinning or weakness (osteoporosis).
- slowed growth in children. A child’s growth should be checked often.
- eye problems including glaucoma, increased pressure in your eye, cataracts, or other changes in vision. You should have regular eye exams while using BREO ELLIPTA.
- changes in laboratory blood values, including high levels of blood sugar (hyperglycemia) and low levels of potassium (hypokalemia).

Common side effects of BREO ELLIPTA include:

COPD:

- runny nose and sore throat
- upper respiratory tract infection
- headache
- thrush in your mouth or throat. Rinse your mouth with water without swallowing after use to help prevent this.
- back pain
- pneumonia

- bronchitis
- inflammation of the sinuses
- cough
- mouth and throat pain
- joint pain
- increased blood pressure
- flu
- fever

Asthma:

- runny nose and sore throat
- thrush in your mouth or throat. Rinse your mouth with water without swallowing after use to help prevent this.
- headache
- flu

- respiratory tract infection
- bronchitis
- inflammation of the sinuses
- mouth and throat pain
- hoarseness and voice changes
- cough

These are not all the possible side effects of BREO ELLIPTA.

Call your doctor for medical advice about side effects. You may report side effects to FDA at 1-800-FDA-1088.

How should I store BREO ELLIPTA?

- Store BREO ELLIPTA at room temperature between 68°F and 77°F (20°C and 25°C). Keep in a dry place away from heat and sunlight.
- Store BREO ELLIPTA in the unopened tray and only open when ready for use.
- Safely throw away BREO ELLIPTA in the trash 6 weeks after you open the tray or when the counter reads “0”, whichever comes first. Write the date you open the tray on the label on the inhaler.

Keep BREO ELLIPTA and all medicines out of the reach of children.

General information about the safe and effective use of BREO ELLIPTA.

Medicines are sometimes prescribed for purposes other than those listed in a Patient Information leaflet. Do not use BREO ELLIPTA for a condition for which it was not prescribed. Do not give BREO ELLIPTA to other people, even if they have the same symptoms that you have. It may harm them.

You can ask your healthcare provider or pharmacist for information about BREO ELLIPTA that is written for health professionals.

What are the ingredients in BREO ELLIPTA?

Active ingredients: fluticasone furoate, vilanterol trifenatate

Inactive ingredients: lactose monohydrate (contains milk proteins), magnesium stearate

For more information about BREO ELLIPTA, call 1-888-825-5249.

Trademarks are owned by or licensed to the GSK group of companies.

BREO ELLIPTA was developed in collaboration with Innoviva.

GlaxoSmithKline, Durham, NC 27701

©2023 GSK group of companies or its licensor.

BRE:7PIL

This Patient Information has been approved by the U.S. Food and Drug Administration Revised: May 2023

INSTRUCTIONS FOR USE

BREO ELLIPTA (BRE-oh e-LIP-ta)

(fluticasone furoate and vilanterol inhalation powder)

for oral inhalation use

Read this before you start:

- If you open and close the cover without inhaling the medicine, you will lose the dose.
- The lost dose will be securely held inside the inhaler, but it will no longer be available to be inhaled.
- It is not possible to accidentally take a double dose or an extra dose in 1 inhalation.

Your BREO ELLIPTA inhaler

How to use your inhaler

- BREO ELLIPTA comes in a tray.
- Peel back the lid to open the tray. See Figure A.
- The tray contains a desiccant to reduce moisture. Do not eat or inhale. Throw it away in the household trash out of reach of children and pets. See Figure B.

Figure A

Figure B

Important Notes:

- Your inhaler contains 30 doses (14 doses if you have a sample or institutional pack).
- Each time you fully open the cover of the inhaler (you will hear a clicking sound), a dose is ready to be inhaled. This is shown by a decrease in the number on the counter.
- If you open and close the cover without inhaling the medicine, you will lose the dose. The lost dose will be held in the inhaler, but it will no longer be available to be inhaled. It is not possible to accidentally take a double dose or an extra dose in 1 inhalation.
- Do not open the cover of the inhaler until you are ready to use it. To avoid wasting doses after the inhaler is ready, do not close the cover until after you have inhaled the medicine.
- Write the “Tray opened” and “Discard” dates on the inhaler label. The “Discard” date is 6 weeks from the date you open the tray.

Check the counter. See Figure C.

Figure C

- Before the inhaler is used for the first time, the counter should show the number 30 (14 if you have a sample or institutional pack). This is the number of doses in the inhaler.
- Each time you open the cover, you prepare 1 dose of medicine.
- The counter counts down by 1 each time you open the cover.

Prepare your dose:

Wait to open the cover until you are ready to take your dose.

Figure D

Step 1. Open the cover of the inhaler. See Figure D.

- Slide the cover down to expose the mouthpiece. You should hear a “click.” The counter will count down by 1 number. You do not need to shake this kind of inhaler. Your inhaler is now ready to use.
- If the counter does not count down as you hear the click, the inhaler will not deliver the medicine. Call your healthcare provider or pharmacist if this happens.

Figure E

Step 2. Breathe out. See Figure E.

- While holding the inhaler away from your mouth, breathe out (exhale) fully. Do not breathe out into the mouthpiece.

Figure F

Step 3. Inhale your medicine. See Figure F.

- Put the mouthpiece between your lips, and close your lips firmly around it. Your lips should fit over the curved shape of the mouthpiece.
- Take one long, steady, deep breath in through your mouth. Do not breathe in through your nose.

Figure G

- Do not block the air vent with your fingers. See Figure G.

Figure H

- Remove the inhaler from your mouth and hold your breath for about 3 to 4 seconds (or as long as comfortable for you). See Figure H.

Figure I

Step 4. Breathe out slowly and gently. See Figure I.

- You may not taste or feel the medicine, even when you are using the inhaler correctly.
- Do not take another dose from the inhaler even if you do not feel or taste the medicine.

Figure J

Step 5. Close the inhaler. See Figure J.

- You can clean the mouthpiece if needed, using a dry tissue, before you close the cover. Routine cleaning is not required.
- Slide the cover up and over the mouthpiece as far as it will go.

Figure K

Step 6. Rinse your mouth. See Figure K.

- Rinse your mouth with water after you have used the inhaler and spit the water out. Do not swallow the water.

Important Note: When should you get a refill?

Figure L

- When you have fewer than 10 doses remaining in your inhaler, the left half of the counter shows red as a reminder to get a refill. See Figure L.
- After you have inhaled the last dose, the counter will show “0” and will be empty.
- Throw the empty inhaler away in your household trash out of reach of children and pets.

For more information about BREO ELLIPTA or how to use your inhaler, call 1-888-825-5249.

Trademarks are owned by or licensed to the GSK group of companies.

BREO ELLIPTA was developed in collaboration with Innoviva.

GlaxoSmithKline, Durham, NC 27701

©2023 GSK group of companies or its licensor.

BRE:4IFU

This Instructions for Use has been approved by the U.S. Food and Drug Administration Revised: May 2023

PACKAGE LABEL

PRINCIPAL DISPLAY PANEL

NDC 0173-0916-10

BREO ELLIPTA

(fluticasone furoate and vilanterol inhalation powder)

50 mcg/25 mcg

Rx Only

FOR ORAL INHALATION ONLY

BREO ELLIPTA contains 2 foil strips of 30 blisters each. Each blister on one strip contains 50 mcg of fluticasone furoate and lactose monohydrate. Each blister on the other strip contains 25 mcg of vilanterol, magnesium stearate, and lactose monohydrate.

1 ELLIPTA Inhaler containing 30 doses (60 blisters total)

GSK

Trademarks are owned by or licensed to the GSK group of Companies. BREO ELLIPTA was developed in collaboration with Innoviva, Inc.

©2023 GSK group of companies or its licensor.

Made in UK

62000000086025 Rev. 5/23

PACKAGE LABEL

PRINCIPAL DISPLAY PANEL

NDC 0173-0859-10

BREO ELLIPTA

(fluticasone furoate and vilanterol inhalation powder)

100 mcg/25 mcg

Rx Only

FOR ORAL INHALATION ONLY

BREO ELLIPTA contains 2 foil strips of 30 blisters each. Each blister on one strip contains 100 mcg of fluticasone furoate and lactose monohydrate. Each blister on the other strip contains 25 mcg of vilanterol, magnesium stearate, and lactose monohydrate.

1 ELLIPTA Inhaler containing 30 doses (60 blisters total)

GSK

Trademarks are owned by or licensed to the GSK group of Companies. BREO ELLIPTA was developed in collaboration with Innoviva, Inc.

©2023 GSK group of companies or its licensor.

Made in UK

62000000089073 Rev. 7/23

PACKAGE LABEL

PRINCIPAL DISPLAY PANEL

NDC 0173-0882-10

BREO ELLIPTA

(fluticasone furoate and vilanterol inhalation powder)

200 mcg/25 mcg

Rx Only

FOR ORAL INHALATION ONLY

BREO ELLIPTA contains 2 foil strips of 30 blisters each. Each blister on one strip contains 200 mcg of fluticasone furoate and lactose monohydrate. Each blister on the other strip contains 25 mcg of vilanterol, magnesium stearate, and lactose monohydrate.

1 ELLIPTA Inhaler containing 30 doses (60 blisters total)

GSK

Trademarks are owned by or licensed to the GSK group of Companies. BREO ELLIPTA was developed in collaboration with Innoviva, Inc.

©2023 GSK group of companies or its licensor.

Made in UK

62000000089082 Rev. 7/23